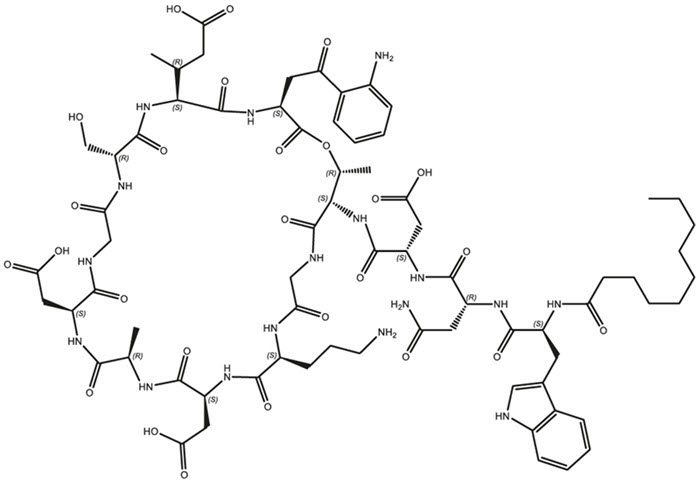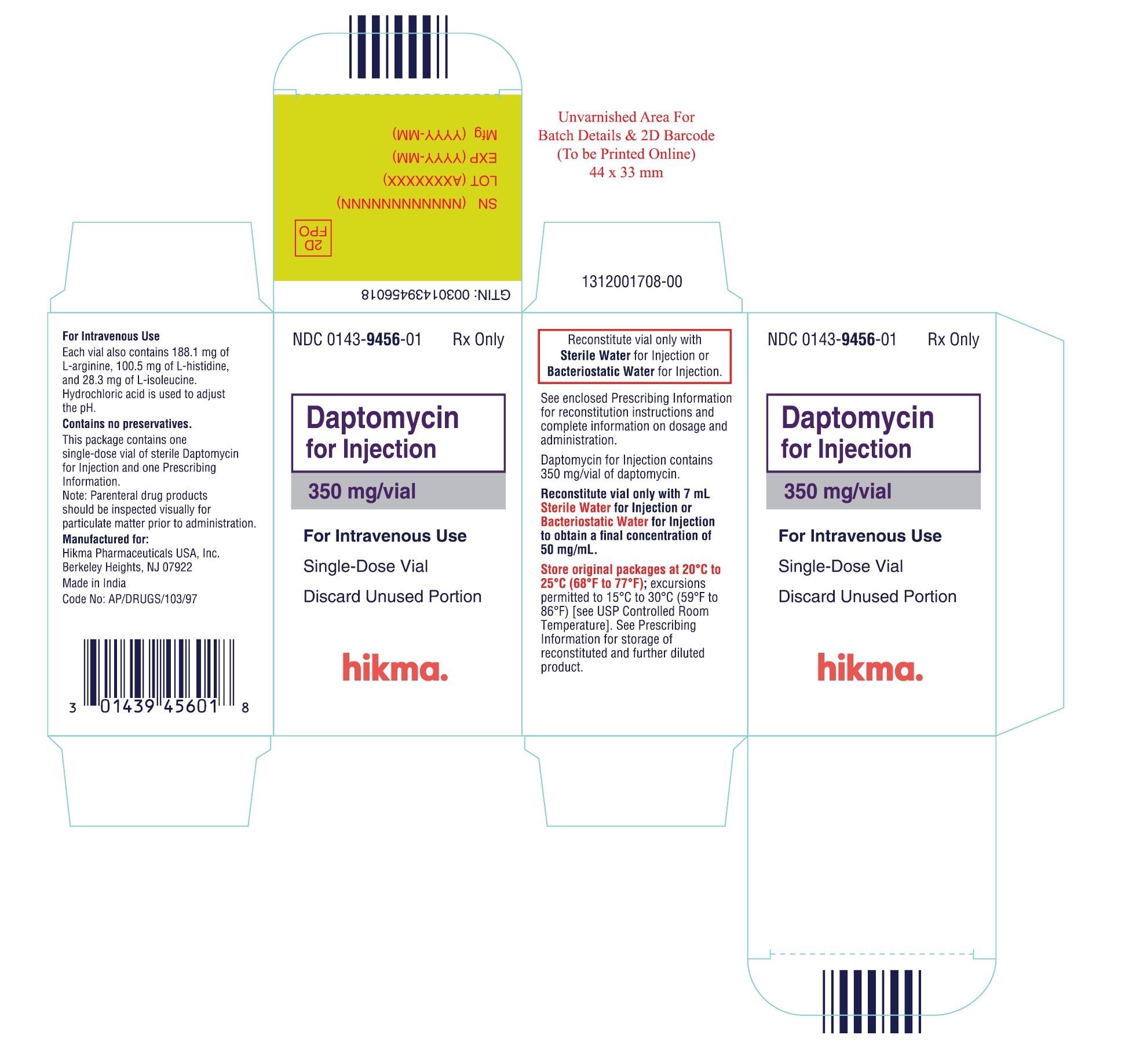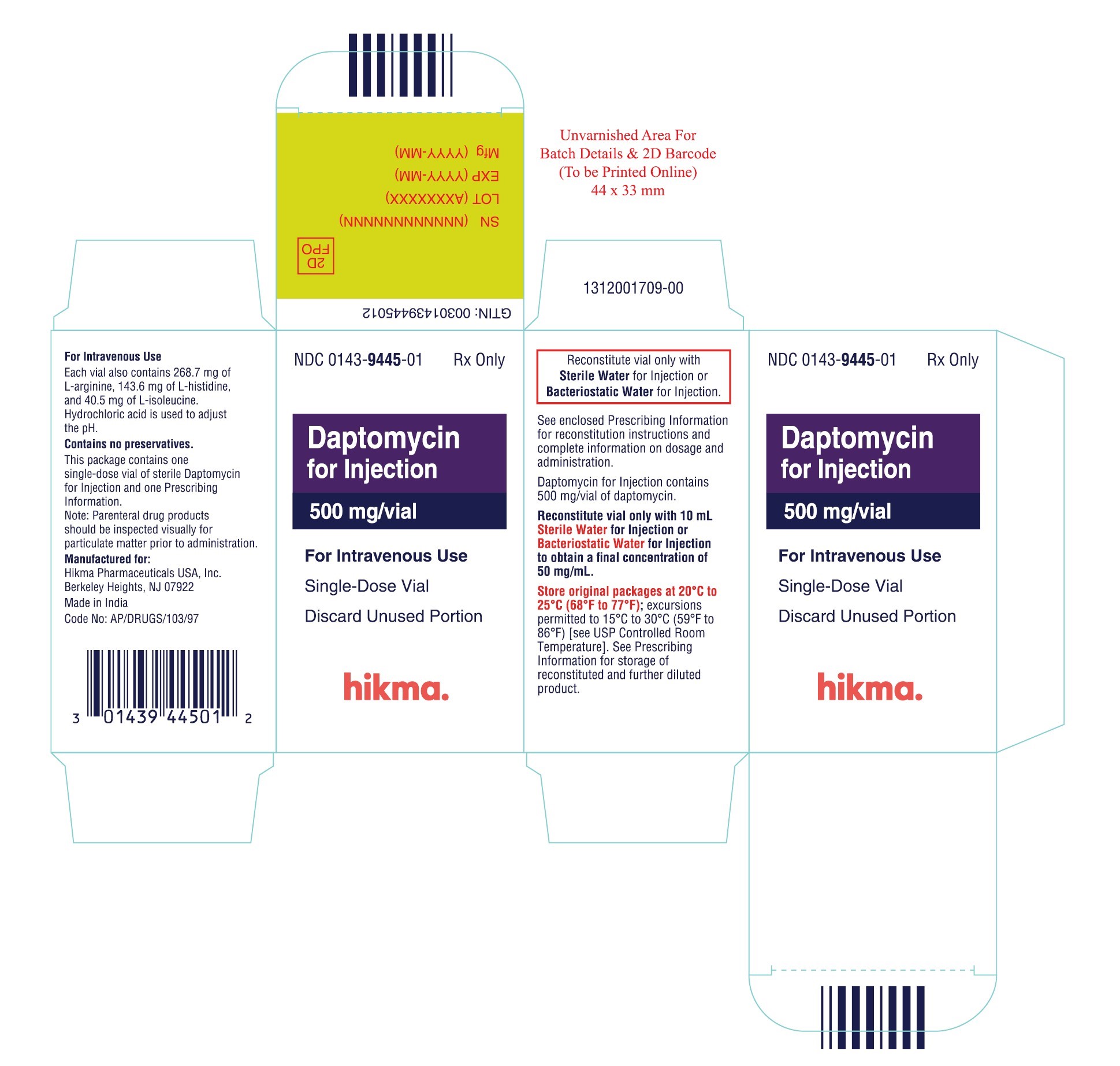 DRUG LABEL: Daptomycin
NDC: 0143-9456 | Form: INJECTION, POWDER, LYOPHILIZED, FOR SOLUTION
Manufacturer: Hikma Pharmaceuticals USA Inc.
Category: prescription | Type: HUMAN PRESCRIPTION DRUG LABEL
Date: 20251218

ACTIVE INGREDIENTS: DAPTOMYCIN 350 mg/7 mL
INACTIVE INGREDIENTS: ARGININE 188.1 mg/7 mL; HISTIDINE 100.5 mg/7 mL; ISOLEUCINE 28.3 mg/7 mL; HYDROCHLORIC ACID

HIGHLIGHTS OF PRESCRIBING INFORMATION

These highlights do not include all the information needed to use DAPTOMYCIN FOR INJECTION safely and effectively. See full prescribing information for DAPTOMYCIN FOR INJECTION.
DAPTOMYCIN for injection, for intravenous use
Initial U.S. Approval: 2003

1 INDICATIONS AND USAGE

Daptomycin for Injection is a lipopeptide antibacterial indicated for the treatment of:

- Complicated skin and skin structure infections (cSSSI) in adult and pediatric patients (1 to 17 years of age) (1.1) and,
- Staphylococcus aureus bloodstream infections (bacteremia), in adult patients including those with right-sided infective endocarditis, (1.2)
- Staphylococcus aureus bloodstream infections (bacteremia) in pediatric patients (1 to 17 years of age). (1.3)

Limitations of Use:

- Daptomycin for Injection is not indicated for the treatment of pneumonia. (1.4)
- Daptomycin for Injection is not indicated for the treatment of left-sided infective endocarditis due to S. aureus. (1.4)
- Daptomycin for Injection is not recommended in pediatric patients younger than one year of age due to the risk of potential effects on muscular, neuromuscular, and/or nervous systems (either peripheral and/or central) observed in neonatal dogs. (1.4)

To reduce the development of drug-resistant bacteria and maintain the effectiveness of Daptomycin for Injection and other antibacterial drugs, Daptomycin for Injection should be used to treat or prevent infections that are proven or strongly suspected to be caused by bacteria. (1.5)

2 DOSAGE AND ADMINISTRATION

Adult Patients

- Administer to adult patients intravenously, either by injection over a 2-minute period or by infusion over a 30-minute period. (2.1, 2.7)
- Recommended dosage regimen for adult patients (2.2, 2.4, 2.6):

Creatinine Clearance (CLCR) | Dosage Regimen
Creatinine Clearance (CLCR) | cSSSI For 7 to 14 days | S. aureus Bacteremia For 2 to 6 weeks
≥30 mL/min | 4 mg/kg once every 24 hours | 6 mg/kg once every 24 hours
<30 mL/min, including hemodialysis and CAPD | 4 mg/kg once every 48 hours [Administered following hemodialysis on hemodialysis days.] | 6 mg/kg once every 48 hours

Pediatric Patients

- Unlike in adults, do NOT administer by injection over a two (2) minute period to pediatric patients. (2.1, 2.7)
- Administer to pediatric patients intravenously by infusion over a 30- or 60-minute period, based on age. (2.1, 2.7)
- Recommended dosage regimen for pediatric patients (1 to 17 years of age) with cSSSI, based on age (2.3):

Age group | Dosage [Recommended dosage is for pediatric patients (1 to 17 years of age) with normal renal function. Dosage adjustment for pediatric patients with renal impairment has not been established.] | Duration of therapy
12 to 17 years | 5 mg/kg once every 24 hours infused over 30 minutes | Up to 14 days
7 to 11 years | 7 mg/kg once every 24 hours infused over 30 minutes | Up to 14 days
2 to 6 years | 9 mg/kg once every 24 hours infused over 60 minutes | Up to 14 days
1 to less than 2 years | 10 mg/kg once every 24 hours infused over 60 minutes | Up to 14 days

- Recommended dosage regimen for pediatric patients (1 to 17 years of age) with S. aureus bacteremia, based on age (2.5):

Age group | Dosage [Recommended dosage is for pediatric patients (1 to 17 years of age) with normal renal function. Dosage adjustment for pediatric patients with renal impairment has not been established.] | Duration of therapy
12 to 17 years | 7 mg/kg once every 24 hours infused over 30 minutes | Up to 42 days
7 to 11 years | 9 mg/kg once every 24 hours infused over 30 minutes | Up to 42 days
1 to 6 years | 12 mg/kg once every 24 hours infused over 60 minutes | Up to 42 days

- There are other formulations of daptomycin that have differences concerning storage and reconstitution. Carefully follow the reconstitution and storage procedures in this labeling. (2.7)
- Do not use in conjunction with ReadyMED® elastomeric infusion pumps in adult and pediatric patients. (2.9)

3 DOSAGE FORMS AND STRENGTHS

- For Injection: 350 mg and 500 mg of daptomycin as a lyophilized powder or cake in a single-dose vial for reconstitution (3)

4 CONTRAINDICATIONS

- Known hypersensitivity to daptomycin. (4)

5 WARNINGS AND PRECAUTIONS

- Anaphylaxis/hypersensitivity reactions (including life-threatening): Discontinue Daptomycin for Injection and treat signs/symptoms. (5.1)
- Myopathy and rhabdomyolysis: Monitor CPK levels and follow muscle pain or weakness; if elevated CPK or myopathy occurs, consider discontinuation of Daptomycin for Injection. (5.2)
- Eosinophilic pneumonia: Discontinue Daptomycin for Injection and consider treatment with systemic steroids. (5.3)
- Drug Reaction with Eosinophilia and Systemic Symptoms (DRESS): Discontinue Daptomycin for Injection and institute appropriate treatment. (5.4)
- Tubulointerstitial Nephritis (TIN): Discontinue Daptomycin for Injection and institute appropriate treatment. (5.5)
- Peripheral neuropathy: Monitor for neuropathy and consider discontinuation. (5.6)
- Potential nervous system and/or muscular system effects in pediatric patients younger than 12 months: Avoid use of Daptomycin for Injection in this age group. (5.7)
- Clostridioides difficile–associated diarrhea: Evaluate patients if diarrhea occurs. (5.8)
- Persisting or relapsing S. aureus bacteremia/endocarditis: Perform susceptibility testing and rule out sequestered foci of infection. (5.9)
- Decreased efficacy was observed in adult patients with moderate baseline renal impairment. (5.10)

6 ADVERSE REACTIONS

- Adult cSSSI Patients: The most common adverse reactions that occurred in ≥2% of adult cSSSI patients receiving daptomycin for injection 4 mg/kg were diarrhea, headache, dizziness, rash, abnormal liver function tests, elevated creatine phosphokinase (CPK), urinary tract infections, hypotension, and dyspnea. (6.1)
- Pediatric cSSSI Patients: The most common adverse reactions that occurred in ≥2% of pediatric patients receiving daptomycin for injection were diarrhea, vomiting, abdominal pain, pruritus, pyrexia, elevated CPK, and headache. (6.1)
- Adult S. aureus bacteremia/endocarditis Patients: The most common adverse reactions that occurred in ≥5% of S. aureus bacteremia/endocarditis patients receiving daptomycin for injection 6 mg/kg were sepsis, bacteremia, abdominal pain, chest pain, edema, pharyngolaryngeal pain, pruritus, increased sweating, insomnia, elevated CPK, and hypertension. (6.1)
- Pediatric S. aureus bacteremia Patients: The most common adverse reactions that occurred in ≥5% of pediatric patients receiving daptomycin for injection were vomiting and elevated CPK. (6.1)

To report SUSPECTED ADVERSE REACTIONS, contact Hikma Pharmaceuticals USA Inc. at 1-877-845-0689 or FDA at 1-800-FDA-1088 or www.fda.gov/medwatch.

FULL PRESCRIBING INFORMATION

1 INDICATIONS AND USAGE

1.1 Complicated Skin and Skin Structure Infections (cSSSI)

Daptomycin for Injection is indicated for the treatment of adult and pediatric patients (1 to 17 years of age) with complicated skin and skin structure infections (cSSSI) caused by susceptible isolates of the following Gram-positive bacteria: Staphylococcus aureus (including methicillin-resistant isolates), Streptococcus pyogenes, Streptococcus agalactiae, Streptococcus dysgalactiae subsp. equisimilis, and Enterococcus faecalis (vancomycin-susceptible isolates only).

1.2 Staphylococcus aureus Bloodstream Infections (Bacteremia) in Adult Patients, Including Those with Right-Sided Infective Endocarditis, Caused by Methicillin-Susceptible and Methicillin-Resistant Isolates

Daptomycin for Injection is indicated for the treatment of adult patients with Staphylococcus aureus bloodstream infections (bacteremia), including adult patients with right-sided infective endocarditis, caused by methicillin-susceptible and methicillin-resistant isolates.

1.3 Staphylococcus aureus Bloodstream Infections (Bacteremia) in Pediatric Patients (1 to 17 Years of Age)

Daptomycin for Injection is indicated for the treatment of pediatric patients (1 to 17 years of age) with Staphylococcus aureus bloodstream infections (bacteremia).

1.4 Limitations of Use

Daptomycin for Injection is not indicated for the treatment of pneumonia.

Daptomycin for Injection is not indicated for the treatment of left-sided infective endocarditis due to S. aureus. The clinical trial of daptomycin for injection in adult patients with S. aureus bloodstream infections included limited data from patients with left-sided infective endocarditis; outcomes in these patients were poor [see Clinical Studies (14.2)]. Daptomycin for injection has not been studied in patients with prosthetic valve endocarditis.

Daptomycin for Injection is not recommended in pediatric patients younger than 1 year of age due to the risk of potential effects on muscular, neuromuscular, and/or nervous systems (either peripheral and/or central) observed in neonatal dogs [see Warnings and Precautions (5.7) and Nonclinical Toxicology (13.2)].

1.5 Usage

Appropriate specimens for microbiological examination should be obtained in order to isolate and identify the causative pathogens and to determine their susceptibility to daptomycin.

To reduce the development of drug-resistant bacteria and maintain the effectiveness of Daptomycin for Injection and other antibacterial drugs, Daptomycin for Injection should be used only to treat or prevent infections that are proven or strongly suspected to be caused by susceptible bacteria.

When culture and susceptibility information is available, it should be considered in selecting or modifying antibacterial therapy. In the absence of such data, local epidemiology and susceptibility patterns may contribute to the empiric selection of therapy. Empiric therapy may be initiated while awaiting test results.

2 DOSAGE AND ADMINISTRATION

2.1 Important Administration Duration Instructions

Adults

Administer the appropriate volume of the reconstituted Daptomycin for Injection (concentration of 50 mg/mL) to adult patients intravenously either by injection over a two (2) minute period or by intravenous infusion over a thirty (30) minute period [see Dosage and Administration (2.2, 2.4, 2.7)].

Pediatric Patients (1 to 17 Years of Age)

Unlike in adults, do NOT administer Daptomycin for Injection by injection over a two (2) minute period to pediatric patients.

- Pediatric Patients 7 to 17 years of Age: Administer Daptomycin for Injection intravenously by infusion over a 30-minute period [see Dosage and Administration (2.3, 2.5, 2.7)].
- Pediatric Patients 1 to 6 years of Age: Administer Daptomycin for Injection intravenously by infusion over a 60-minute period [see Dosage and Administration (2.3, 2.5, 2.7)].

2.2 Dosage in Adults for cSSSI

Administer Daptomycin for Injection 4 mg/kg to adult patients intravenously once every 24 hours for 7 to 14 days.

2.3 Dosage in Pediatric Patients (1 to 17 Years of Age) for cSSSI

The recommended dosage regimens based on age for pediatric patients with cSSSI are shown in Table 1. Administer Daptomycin for Injection intravenously once every 24 hours for up to 14 days.

Table 1: Recommended Dosage of Daptomycin for Injection in Pediatric Patients (1 to 17 Years of Age) with cSSSI, Based on Age
Age Range | Dosage Regimen [Recommended dosage regimen is for pediatric patients (1 to 17 years of age) with normal renal function. Dosage adjustment for pediatric patients with renal impairment has not been established.] | Duration of therapy
12 to 17 years | 5 mg/kg once every 24 hours infused over 30 minutes | Up to 14 days
7 to 11 years | 7 mg/kg once every 24 hours infused over 30 minutes | Up to 14 days
2 to 6 years | 9 mg/kg once every 24 hours infused over 60 minutes | Up to 14 days
1 to less than 2 years | 10 mg/kg once every 24 hours infused over 60 minutes | Up to 14 days

2.4 Dosage in Adult Patients with Staphylococcus aureus Bloodstream Infections (Bacteremia), Including Those with Right-Sided Infective Endocarditis, Caused by Methicillin-Susceptible and Methicillin-Resistant Isolates

Administer Daptomycin for Injection 6 mg/kg to adult patients intravenously once every 24 hours for 2 to 6 weeks. There are limited safety data for the use of daptomycin for injection for more than 28 days of therapy. In the Phase 3 trial, there were a total of 14 adult patients who were treated with daptomycin for injection for more than 28 days.

2.5 Dosage in Pediatric Patients (1 to 17 Years of Age) with Staphylococcus aureus Bloodstream Infections (Bacteremia)

The recommended dosage regimens based on age for pediatric patients with S. aureus bloodstream infections (bacteremia) are shown in Table 2. Administer Daptomycin for Injection intravenously in 0.9% sodium chloride injection once every 24 hours for up to 42 days.

Table 2: Recommended Dosage of Daptomycin for Injection in Pediatric Patients (1 to 17 Years of Age) with S. aureus Bacteremia, Based on Age
Age group | Dosage [Recommended dosage is for pediatric patients (1 to 17 years of age) with normal renal function. Dosage adjustment for pediatric patients with renal impairment has not been established.] | Duration of therapy
12 to 17 years | 7 mg/kg once every 24 hours infused over 30 minutes | Up to 42 days
7 to 11 years | 9 mg/kg once every 24 hours infused over 30 minutes | Up to 42 days
1 to 6 years | 12 mg/kg once every 24 hours infused over 60 minutes | Up to 42 days

2.6 Dosage in Patients with Renal Impairment

Adult Patients:

No dosage adjustment is required in adult patients with creatinine clearance (CLCR) greater than or equal to 30 mL/min. The recommended dosage regimen for Daptomycin for Injection in adult patients with CLCR less than 30 mL/min, including adult patients on hemodialysis or continuous ambulatory peritoneal dialysis (CAPD), is 4 mg/kg (cSSSI) or 6 mg/kg (S. aureus bloodstream infections) once every 48 hours (Table 3). When possible, Daptomycin for Injection should be administered following the completion of hemodialysis on hemodialysis days [see Warnings and Precautions (5.2, 5.10), Use in Specific Populations (8.6), and Clinical Pharmacology (12.3)].

Table 3: Recommended Dosage of Daptomycin for Injection in Adult Patients
Creatinine Clearance (CLCR) | Dosage Regimen in Adults
Creatinine Clearance (CLCR) | cSSSI | S. aureus Bloodstream Infections
Greater than or equal to 30 mL/min | 4 mg/kg once every 24 hours | 6 mg/kg once every 24 hours
Less than 30 mL/min, including hemodialysis and CAPD | 4 mg/kg once every 48 hours [When possible, administer Daptomycin for Injection following the completion of hemodialysis on hemodialysis days.] | 6 mg/kg once every 48 hours

Pediatric Patients:

The dosage regimen for Daptomycin for Injection in pediatric patients with renal impairment has not been established.

2.7 Preparation and Administration of Daptomycin for Injection

There are other formulations of daptomycin that have differences concerning reconstitution and storage. Carefully follow the reconstitution and storage procedures described in this labeling.

Reconstitution of Daptomycin for Injection Vial

Daptomycin for Injection must be reconstituted within the vial only with either Sterile Water for Injection or Bacteriostatic Water for Injection.

Do NOT use saline based diluents for the reconstitution in the vial because this will result in a hyperosmotic solution that may result in infusion site reactions if the reconstituted product is administered as an intravenous injection over a period of 2 minutes.

Daptomycin for Injection is supplied in single-dose vials, each containing 350 mg or 500 mg daptomycin as a sterile, lyophilized powder. The contents of a Daptomycin for Injection vial should be reconstituted, using aseptic technique, to 50 mg/mL as follows:

1. Remove the polypropylene flip-off cap from the Daptomycin for Injection vial to expose the central portion of the rubber stopper.
2. Wipe the top of the rubber stopper with an alcohol swab or other antiseptic solution and allow to dry. After cleaning, do not touch the rubber stopper or allow it to touch any other surface.
3. Transfer 7 mL of Sterile Water for Injection or Bacteriostatic Water for Injection through the center of the rubber stopper into the Daptomycin for Injection 350 mg vial or 10 mL of Sterile Water for Injection or Bacteriostatic Water for Injection through the center of the rubber stopper into the Daptomycin for Injection, 500 mg vial. Use a beveled sterile transfer needle that is 21 gauge or smaller in diameter, pointing the transfer needle toward the wall of the vial.
4. Rotate or swirl the vial contents for a few minutes, as needed, to obtain a completely reconstituted solution.

Administration Instructions

Parenteral drug products should be inspected visually for particulate matter prior to administration.

Slowly remove reconstituted liquid (50 mg daptomycin/mL) from the vial using a beveled sterile needle that is 21 gauge or smaller in diameter. Administer as an intravenous injection or infusion as described below:

Adults

Intravenous Injection over a period of 2 minutes

- For intravenous (IV) injection over a period of 2 minutes in adult patients only: Administer the appropriate volume of the reconstituted Daptomycin for Injection (concentration of 50 mg/mL).

Intravenous Infusion over a period of 30 minutes

- For IV infusion over a period of 30 minutes in adult patients: The appropriate volume of the reconstituted Daptomycin for Injection (concentration of 50 mg/mL) should be further diluted, using aseptic technique, into a 50 mL IV infusion bag containing 0.9% sodium chloride injection.

Pediatric Patients (1 to 17 Years of Age)

Intravenous Infusion over a period of 30 or 60 minutes

- Unlike in Adults, do NOT administer Daptomycin for Injection by injection over a two (2) minute period to pediatric patients [see Dosage and Administration (2.1)].
- For Intravenous infusion over a period of 60 minutes in pediatric patients 1 to 6 years of age: The appropriate volume of the reconstituted Daptomycin for Injection (concentration of 50 mg/mL) should be further diluted, using aseptic technique, into an intravenous infusion bag containing 25 mL of 0.9% sodium chloride injection. The infusion rate should be maintained at 0.42 mL/minute over the 60-minute period.
- For Intravenous infusion over a period of 30 minutes in pediatric patients 7 to 17 years of age: The appropriate volume of the reconstituted Daptomycin for Injection (concentration of 50 mg/mL) should be further diluted, using aseptic technique, into a 50 mL IV infusion bag containing 0.9% sodium chloride injection. The infusion rate should be maintained at 1.67 mL/minute over the 30-minute period.

No preservative or bacteriostatic agent is present in this product. Aseptic technique must be used in the preparation of final IV solution. Table 4 below provides in-use storage conditions for reconstituted Daptomycin for Injection in acceptable intravenous diluents in the syringe, vial and intravenous bag (for reconstitution and dilution). Do not exceed the listed shelf-life of reconstituted and diluted solutions of Daptomycin for Injection. Discard unused portions of Daptomycin for Injection.

Table 4: In-Use Storage Conditions for Daptomycin for Injection Once Reconstituted in Acceptable Intravenous Diluents
Container | Diluent | In-Use Shelf-Life
Container | Diluent | Room Temperature (20°C to 25°C, 68°F to 77°F) | Refrigerated (2°C to 8°C, 36°F to 46°F)
Vial | Sterile Water for Injection | 1 Day | 3 Days
Vial | Bacteriostatic Water for Injection | 2 Days | 3 Days
Syringe [Polypropylene syringe with elastomeric plunger stopper.] | Sterile Water for Injection | 1 Day | 3 Days
Syringe [Polypropylene syringe with elastomeric plunger stopper.] | Bacteriostatic Water for Injection | 2 Days | 5 Days
Intravenous Bag | Vial reconstituted with Sterile Water for Injection and immediately diluted with 0.9% sodium chloride injection | 19 Hours | 3 Days
Intravenous Bag | Vial reconstituted with Bacteriostatic Water for Injection and immediately diluted with 0.9% sodium chloride injection | 2 Days | 5 Days

2.8 Compatible Intravenous Solutions

Reconstituted Daptomycin for Injection is compatible with Sterile Water for Injection, Bacteriostatic Water for Injection, and 0.9% sodium chloride injection. [See Dosage and Administration (2.7).]

2.9 Incompatibilities

Daptomycin for Injection is not compatible with dextrose-containing diluents.

Daptomycin for Injection should not be used in conjunction with ReadyMED® elastomeric infusion pumps. Stability studies of daptomycin for injection solutions stored in ReadyMED® elastomeric infusion pumps identified an impurity (2-mercaptobenzothiazole) leaching from this pump system into the daptomycin for injection solution.

Because only limited data are available on the compatibility of Daptomycin for Injection with other IV substances, additives and other medications should not be added to Daptomycin for Injection single-dose vials or infusion bags or infused simultaneously with Daptomycin for Injection through the same IV line. If the same IV line is used for sequential infusion of different drugs, the line should be flushed with a compatible intravenous solution before and after infusion with Daptomycin for Injection.

3 DOSAGE FORMS AND STRENGTHS

For Injection: 350 mg or 500 mg daptomycin as a sterile, pale yellow to light brown lyophilized powder or cake in a single-dose vial for reconstitution.

4 CONTRAINDICATIONS

Daptomycin for Injection is contraindicated in patients with known hypersensitivity to daptomycin [see Warnings and Precautions (5.1)].

5 WARNINGS AND PRECAUTIONS

5.1 Anaphylaxis/Hypersensitivity Reactions

Anaphylaxis/hypersensitivity reactions have been reported with the use of antibacterial agents, including daptomycin for injection, and may be life-threatening. If an allergic reaction to Daptomycin for Injection occurs, discontinue the drug and institute appropriate therapy [see Adverse Reactions (6.2)].

5.2 Myopathy and Rhabdomyolysis

Myopathy, defined as muscle aching or muscle weakness in conjunction with increases in creatine phosphokinase (CPK) values to greater than 10 times the upper limit of normal (ULN), has been reported with the use of daptomycin for injection. Rhabdomyolysis, with or without acute renal failure, has been reported [see Adverse Reactions (6.2)].

Patients receiving Daptomycin for Injection should be monitored for the development of muscle pain or weakness, particularly of the distal extremities. In patients who receive Daptomycin for Injection, CPK levels should be monitored weekly, and more frequently in patients who received recent prior or concomitant therapy with an HMG-CoA reductase inhibitor or in whom elevations in CPK occur during treatment with Daptomycin for Injection.

In adult patients with renal impairment, both renal function and CPK should be monitored more frequently than once weekly [see Use in Specific Populations (8.6) and Clinical Pharmacology (12.3)].

In Phase 1 studies and Phase 2 clinical trials in adults, CPK elevations appeared to be more frequent when daptomycin for injection was dosed more than once daily. Therefore, Daptomycin for Injection should not be dosed more frequently than once a day.

Daptomycin for Injection should be discontinued in patients with unexplained signs and symptoms of myopathy in conjunction with CPK elevations to levels >1,000 U/L (~5× ULN), and in patients without reported symptoms who have marked elevations in CPK, with levels >2,000 U/L (≥10× ULN).

In addition, consideration should be given to suspending agents associated with rhabdomyolysis, such as HMG-CoA reductase inhibitors, temporarily in patients receiving Daptomycin for Injection [see Drug Interactions (7.1)].

5.3 Eosinophilic Pneumonia

Eosinophilic pneumonia has been reported in patients receiving daptomycin for injection [see Adverse Reactions (6.2)]. In reported cases associated with daptomycin for injection, patients developed fever, dyspnea with hypoxic respiratory insufficiency, and diffuse pulmonary infiltrates or organizing pneumonia. In general, patients developed eosinophilic pneumonia 2 to 4 weeks after starting daptomycin for injection and improved when daptomycin for injection was discontinued and steroid therapy was initiated. Recurrence of eosinophilic pneumonia upon re-exposure has been reported. Patients who develop these signs and symptoms while receiving Daptomycin for Injection should undergo prompt medical evaluation, and Daptomycin for Injection should be discontinued immediately. Treatment with systemic steroids is recommended.

5.4 Drug Reaction with Eosinophilia and Systemic Symptoms (DRESS)

DRESS has been reported in post-marketing experience with daptomycin for injection [see Adverse Reactions (6.2)]. Patients who develop skin rash, fever, peripheral eosinophilia, and systemic organ (for example, hepatic, renal, pulmonary) impairment while receiving Daptomycin for Injection should undergo medical evaluation. If DRESS is suspected, discontinue Daptomycin for Injection promptly and institute appropriate treatment.

5.5 Tubulointerstitial Nephritis (TIN)

TIN has been reported in post-marketing experience with daptomycin for injection [see Adverse Reactions (6.2)]. Patients who develop new or worsening renal impairment while receiving Daptomycin for Injection should undergo medical evaluation. If TIN is suspected, discontinue Daptomycin for Injection promptly and institute appropriate treatment.

5.6 Peripheral Neuropathy

Cases of peripheral neuropathy have been reported during the daptomycin for injection postmarketing experience [see Adverse Reactions (6.2)]. Therefore, physicians should be alert to signs and symptoms of peripheral neuropathy in patients receiving Daptomycin for Injection. Monitor for neuropathy and consider discontinuation.

5.7 Potential Nervous System and/or Muscular System Effects in Pediatric Patients Younger than 12 Months

Avoid use of Daptomycin for Injection in pediatric patients younger than 12 months due to the risk of potential effects on muscular, neuromuscular, and/or nervous systems (either peripheral and/or central) observed in neonatal dogs with intravenous daptomycin [see Nonclinical Toxicology (13.2)].

5.8 Clostridioides difficile-Associated Diarrhea

Clostridioides difficile–associated diarrhea (CDAD) has been reported with the use of nearly all systemic antibacterial agents, including Daptomycin for Injection, and may range in severity from mild diarrhea to fatal colitis [see Adverse Reactions (6.2)]. Treatment with antibacterial agents alters the normal flora of the colon, leading to overgrowth of C. difficile.

C. difficile produces toxins A and B, which contribute to the development of CDAD. Hypertoxin-producing strains of C. difficile cause increased morbidity and mortality since these infections can be refractory to antimicrobial therapy and may require colectomy. CDAD must be considered in all patients who present with diarrhea following antibacterial use. Careful medical history is necessary because CDAD has been reported to occur more than 2 months after the administration of antibacterial agents.

If CDAD is suspected or confirmed, ongoing antibacterial use not directed against C. difficile may need to be discontinued. Appropriate fluid and electrolyte management, protein supplementation, antibacterial treatment of C. difficile, and surgical evaluation should be instituted as clinically indicated.

5.9 Persisting or Relapsing S. aureus Bacteremia/Endocarditis

Patients with persisting or relapsing S. aureus bacteremia/endocarditis or poor clinical response should have repeat blood cultures. If a blood culture is positive for S. aureus, minimum inhibitory concentration (MIC) susceptibility testing of the isolate should be performed using a standardized procedure, and diagnostic evaluation of the patient should be performed to rule out sequestered foci of infection. Appropriate surgical intervention (e.g., debridement, removal of prosthetic devices, valve replacement surgery) and/or consideration of a change in antibacterial regimen may be required.

Failure of treatment due to persisting or relapsing S. aureus bacteremia/endocarditis may be due to reduced daptomycin susceptibility (as evidenced by increasing MIC of the S. aureus isolate) [see Clinical Studies (14.2)].

5.10 Decreased Efficacy in Patients with Moderate Baseline Renal Impairment

Limited data are available from the two Phase 3 complicated skin and skin structure infection (cSSSI) trials regarding clinical efficacy of daptomycin for injection treatment in adult patients with creatinine clearance (CLCR) <50 mL/min; only 31/534 (6%) patients treated with daptomycin for injection in the intent-to-treat (ITT) population had a baseline CLCR <50 mL/min. Table 5 shows the number of adult patients by renal function and treatment group who were clinical successes in the Phase 3 cSSSI trials.

Table 5: Clinical Success Rates by Renal Function and Treatment Group in Phase 3 cSSSI Trials in Adult Patients (Population: ITT)
CLCR | Success Rate n/N (%)
CLCR | Daptomycin for Injection 4 mg/kg every 24h | Comparator
50-70 mL/min | 25/38 (66%) | 30/48 (63%)
30-<50 mL/min | 7/15 (47%) | 20/35 (57%)

In a subgroup analysis of the ITT population in the Phase 3 S. aureus bacteremia/endocarditis trial, clinical success rates, as determined by a treatment-blinded Adjudication Committee [see Clinical Studies (14.2)], in the daptomycin for injection-treated adult patients were lower in patients with baseline CLCR <50 mL/min (see Table 6). A decrease of the magnitude shown in Table 6 was not observed in comparator-treated patients.

Table 6: Adjudication Committee Clinical Success Rates at Test of Cure by Baseline Creatinine Clearance and Treatment Subgroup in the S. aureus Bacteremia/Endocarditis Trial in Adult Patients (Population: ITT)
Baseline CLCR | Success Rate n/N (%)
Baseline CLCR | Daptomycin for Injection 6 mg/kg every 24h |  | Comparator
Baseline CLCR | Bacteremia | Right-Sided Infective Endocarditis | Bacteremia | Right-Sided Infective Endocarditis
>80 mL/min | 30/50 (60%) | 7/14 (50%) | 19/42 (45%) | 5/11 (46%)
50–80 mL/min | 12/26 (46%) | 1/4 (25%) | 13/31 (42%) | 1/2 (50%)
30–<50 mL/min | 2/14 (14%) | 0/1 (0%) | 7/17 (41%) | 1/1 (100%)

Consider these data when selecting antibacterial therapy for use in adult patients with baseline moderate to severe renal impairment.

5.11 Increased International Normalized Ratio (INR)/Prolonged Prothrombin Time

Clinically relevant plasma concentrations of daptomycin have been observed to cause a significant concentration-dependent false prolongation of prothrombin time (PT) and elevation of International Normalized Ratio (INR) when certain recombinant thromboplastin reagents are utilized for the assay [see Drug Interactions (7.2)].

5.12 Development of Drug-Resistant Bacteria

Prescribing Daptomycin for Injection in the absence of a proven or strongly suspected bacterial infection or a prophylactic indication is unlikely to provide benefit to the patient and increases the risk of the development of drug-resistant bacteria.

6 ADVERSE REACTIONS

The following adverse reactions are described, or described in greater detail, in other sections:

- Anaphylaxis/Hypersensitivity Reactions [see Warnings and Precautions (5.1)]
- Myopathy and Rhabdomyolysis [see Warnings and Precautions (5.2)]
- Eosinophilic Pneumonia [see Warnings and Precautions (5.3)]
- Drug Reaction with Eosinophilia and Systemic Symptoms [see Warnings and Precautions (5.4)]
- Tubulointerstitial Nephritis [see Warnings and Precautions (5.5)]
- Peripheral Neuropathy [see Warnings and Precautions (5.6)]
- Increased International Normalized Ratio (INR)/Prolonged Prothrombin Time [see Warnings and Precautions (5.11) and Drug Interactions (7.2)]

6.1 Clinical Trials Experience

Because clinical trials are conducted under widely varying conditions, adverse reaction rates observed in the clinical trials of a drug cannot be directly compared with rates in the clinical trials of another drug and may not reflect the rates observed in practice.

Clinical Trial Experience in Adult Patients

Clinical trials enrolled 1,864 adult patients treated with daptomycin for injection and 1,416 treated with comparator.

Complicated Skin and Skin Structure Infection Trials in Adults

In Phase 3 complicated skin and skin structure infection (cSSSI) trials in adult patients, daptomycin for injection was discontinued in 15/534 (2.8%) patients due to an adverse reaction, while comparator was discontinued in 17/558 (3.0%) patients.

The rates of the most common adverse reactions, organized by body system, observed in adult patients with cSSSI (receiving 4 mg/kg daptomycin for injection) are displayed in Table 7.

Table 7: Incidence of Adverse Reactions that Occurred in ≥2% of Adult Patients in the Daptomycin for Injection Treatment Group and ≥ the Comparator Treatment Group in Phase 3 cSSSI Trials
Adverse Reaction | Adult Patients (%)
Adverse Reaction | Daptomycin for Injection 4 mg/kg (N=534) | Comparator [Comparator: vancomycin (1 g IV q12h) or an anti-staphylococcal semi-synthetic penicillin (i.e., nafcillin, oxacillin, cloxacillin, or flucloxacillin; 4 to 12 g/day IV in divided doses).] (N=558)
Gastrointestinal disorders
Diarrhea | 5.2 | 4.3
Nervous system disorders
Headache | 5.4 | 5.4
Dizziness | 2.2 | 2.0
Skin/subcutaneous disorders
Rash | 4.3 | 3.8
Diagnostic investigations
Abnormal liver function tests | 3.0 | 1.6
Elevated CPK | 2.8 | 1.8
Infections
Urinary tract infections | 2.4 | 0.5
Vascular disorders
Hypotension | 2.4 | 1.4
Respiratory disorders
Dyspnea | 2.1 | 1.6

Drug-related adverse reactions (possibly or probably drug-related) that occurred in <1% of adult patients receiving daptomycin for injection in the cSSSI trials are as follows:

Body as a Whole: fatigue, weakness, rigors, flushing, hypersensitivity

Blood/Lymphatic System: leukocytosis, thrombocytopenia, thrombocytosis, eosinophilia, increased International Normalized Ratio (INR)

Cardiovascular System: supraventricular arrhythmia

Dermatologic System: eczema

Digestive System: abdominal distension, stomatitis, jaundice, increased serum lactate dehydrogenase

Metabolic/Nutritional System: hypomagnesemia, increased serum bicarbonate, electrolyte disturbance

Musculoskeletal System: myalgia, muscle cramps, muscle weakness, arthralgia

Nervous System: vertigo, mental status change, paresthesia

Special Senses: taste disturbance, eye irritation

S. aureus Bacteremia/Endocarditis Trial in Adults

In the S. aureus bacteremia/endocarditis trial involving adult patients, daptomycin for injection was discontinued in 20/120 (16.7%) patients due to an adverse reaction, while comparator was discontinued in 21/116 (18.1%) patients.

Serious Gram-negative infections (including bloodstream infections) were reported in 10/120 (8.3%) daptomycin for injection-treated patients and 0/115 comparator-treated patients. Comparator-treated patients received dual therapy that included initial gentamicin for 4 days. Infections were reported during treatment and during early and late follow-up. Gram-negative infections included cholangitis, alcoholic pancreatitis, sternal osteomyelitis/mediastinitis, bowel infarction, recurrent Crohn's disease, recurrent line sepsis, and recurrent urosepsis caused by a number of different Gram-negative bacteria.

The rates of the most common adverse reactions, organized by System Organ Class (SOC), observed in adult patients with S. aureus bacteremia/endocarditis (receiving 6 mg/kg daptomycin for injection) are displayed in Table 8.

Table 8: Incidence of Adverse Reactions that Occurred in ≥5% of Adult Patients in the Daptomycin for Injection Treatment Group and ≥ the Comparator Treatment Group in the S. aureus Bacteremia/Endocarditis Trial
Adverse Reaction [NOS, not otherwise specified.] | Adult Patients n (%)
Adverse Reaction [NOS, not otherwise specified.] | Daptomycin for Injection 6 mg/kg (N=120) | Comparator [Comparator: vancomycin (1 g IV q12h) or an anti-staphylococcal semi-synthetic penicillin (i.e., nafcillin, oxacillin, cloxacillin, or flucloxacillin; 2 g IV q4h), each with initial low-dose gentamicin.] (N=116)
Infections and infestations
Sepsis NOS | 6 (5%) | 3 (3%)
Bacteremia | 6 (5%) | 0 (0%)
Gastrointestinal disorders
Abdominal pain NOS | 7 (6%) | 4 (3%)
General disorders and administration site conditions
Chest pain | 8 (7%) | 7 (6%)
Edema NOS | 8 (7%) | 5 (4%)
Respiratory, thoracic and mediastinal disorders
Pharyngolaryngeal pain | 10 (8%) | 2 (2%)
Skin and subcutaneous tissue disorders
Pruritus | 7 (6%) | 6 (5%)
Sweating increased | 6 (5%) | 0 (0%)
Psychiatric disorders
Insomnia | 11 (9%) | 8 (7%)
Investigations
Blood creatine phosphokinase increased | 8 (7%) | 1 (1%)
Vascular disorders
Hypertension NOS | 7 (6%) | 3 (3%)

The following reactions, not included above, were reported as possibly or probably drug-related in the daptomycin for injection-treated group:

Blood and Lymphatic System Disorders: eosinophilia, lymphadenopathy, thrombocythemia, thrombocytopenia

Cardiac Disorders: atrial fibrillation, atrial flutter, cardiac arrest

Ear and Labyrinth Disorders: tinnitus

Eye Disorders: vision blurred

Gastrointestinal Disorders: dry mouth, epigastric discomfort, gingival pain, hypoesthesia oral

Infections and Infestations: candidal infection NOS, vaginal candidiasis, fungemia, oral candidiasis, urinary tract infection fungal

Investigations: blood phosphorous increased, blood alkaline phosphatase increased, INR increased, liver function test abnormal, alanine aminotransferase increased, aspartate aminotransferase increased, prothrombin time prolonged

Metabolism and Nutrition Disorders: appetite decreased NOS

Musculoskeletal and Connective Tissue Disorders: myalgia

Nervous System Disorders: dyskinesia, paresthesia

Psychiatric Disorders: hallucination NOS

Renal and Urinary Disorders: proteinuria, renal impairment NOS

Skin and Subcutaneous Tissue Disorders: pruritus generalized, rash vesicular

Other Trials in Adults

In Phase 3 trials of community-acquired pneumonia (CAP) in adult patients, the death rate and rates of serious cardiorespiratory adverse events were higher in daptomycin for injection-treated patients than in comparator-treated patients. These differences were due to lack of therapeutic effectiveness of daptomycin for injection in the treatment of CAP in patients experiencing these adverse events [see Indications and Usage (1.4)].

Laboratory Changes in Adults

Complicated Skin and Skin Structure Infection Trials in Adults

In Phase 3 cSSSI trials of adult patients receiving daptomycin for injection at a dose of 4 mg/kg, elevations in CPK were reported as clinical adverse events in 15/534 (2.8%) daptomycin for injection-treated patients, compared with 10/558 (1.8%) comparator-treated patients. Of the 534 patients treated with daptomycin for injection, 1 (0.2%) had symptoms of muscle pain or weakness associated with CPK elevations to greater than 4 times the upper limit of normal (ULN). The symptoms resolved within 3 days and CPK returned to normal within 7 to 10 days after treatment was discontinued [see Warnings and Precautions (5.2)]. Table 9 summarizes the CPK shifts from Baseline through End of Therapy in the cSSSI adult trials.

Table 9: Incidence of CPK Elevations from Baseline during Therapy in Either the Daptomycin for Injection Treatment Group or the Comparator Treatment Group in Phase 3 cSSSI Adult Trials
Change in CPK |  | All Adult Patients |  |  |  | Adult Patients with Normal CPK at Baseline
Change in CPK |  | Daptomycin for Injection 4 mg/kg (N=430) |  | Comparator [Comparator: vancomycin (1 g IV q12h) or an anti-staphylococcal semi-synthetic penicillin (i.e., nafcillin, oxacillin, cloxacillin, or flucloxacillin; 4 to 12 g/day IV in divided doses).] (N=459) |  | Daptomycin for Injection 4 mg/kg (N=374) |  | Comparator (N=392)
Change in CPK |  | % | n | % | n | % | n | % | n
No Increase |  | 90.7 | 390 | 91.1 | 418 | 91.2 | 341 | 91.1 | 357
Maximum Value | >1× ULN [ULN (Upper Limit of Normal) is defined as 200 U/L.] | 9.3 | 40 | 8.9 | 41 | 8.8 | 33 | 8.9 | 35
 | >2× ULN | 4.9 | 21 | 4.8 | 22 | 3.7 | 14 | 3.1 | 12
 | >4× ULN | 1.4 | 6 | 1.5 | 7 | 1.1 | 4 | 1.0 | 4
 | >5× ULN | 1.4 | 6 | 0.4 | 2 | 1.1 | 4 | 0.0 | 0
 | >10× ULN | 0.5 | 2 | 0.2 | 1 | 0.2 | 1 | 0.0 | 0
Note: Elevations in CPK observed in adult patients treated with daptomycin for injection or comparator were not clinically or statistically significantly different.

S. aureus Bacteremia/Endocarditis Trial in Adults

In the S. aureus bacteremia/endocarditis trial in adult patients, at a dose of 6 mg/kg, 11/120 (9.2%) daptomycin for injection-treated patients, including two patients with baseline CPK levels >500 U/L, had CPK elevations to levels >500 U/L, compared with 1/116 (0.9%) comparator-treated patients. Of the 11 daptomycin for injection-treated patients, 4 had prior or concomitant treatment with an HMG-CoA reductase inhibitor. Three of these 11 daptomycin for injection-treated patients discontinued therapy due to CPK elevation, while the one comparator-treated patient did not discontinue therapy [see Warnings and Precautions (5.2)].

Clinical Trial Experience in Pediatric Patients

Complicated Skin and Skin Structure Infection Trial in Pediatric Patients

The safety of daptomycin for injection was evaluated in one clinical trial (in cSSSI), which included 256 pediatric patients (1 to 17 years of age) treated with intravenous daptomycin for injection and 133 patients treated with comparator agents. Patients were given age-dependent doses once daily for a treatment period of up to 14 days (median treatment period was 3 days). The doses given by age group were as follows: 10 mg/kg for 1 to <2 years, 9 mg/kg for 2 to 6 years, 7 mg/kg for 7 to 11 years and 5 mg/kg for 12 to 17 years of age [see Clinical Studies (14)]. Patients treated with daptomycin for injection were (51%) male, (49%) female and (46%) Caucasian and (32%) Asian.

Adverse Reactions Leading to Discontinuation

In the cSSSI study, daptomycin for injection was discontinued in 7/256 (2.7%) patients due to an adverse reaction, while comparator was discontinued in 7/133 (5.3%) patients.

Most Common Adverse Reactions

The rates of the most common adverse reactions, organized by body system, observed in these pediatric patients with cSSSI are displayed in Table 10.

Table 10: Adverse Reactions that Occurred in ≥2% of Pediatric Patients in the Daptomycin for Injection Treatment-Arm and Greater Than or Equal to the Comparator Treatment-Arm in the cSSSI Pediatric Trial
Adverse Reaction | Daptomycin for Injection (N = 256) | Comparator [Comparators included intravenous therapy with either vancomycin, clindamycin, or an anti-staphylococcal semi-synthetic penicillin (nafcillin, oxacillin or cloxacillin)] (N = 133)
Adverse Reaction | n (%) | n (%)
Gastrointestinal disorders
Diarrhea | 18 (7.0) | 7 (5.3)
Vomiting | 7 (2.7) | 1 (0.8)
Abdominal Pain | 5 (2.0) | 0
Skin and subcutaneous tissue disorders
Pruritus | 8 (3.1) | 2 (1.5)
General disorders and administration site conditions
Pyrexia | 10 (3.9) | 4 (3.0)
Investigations
Blood CPK increased | 14 (5.5) | 7 (5.3)
Nervous system disorders
Headache | 7 (2.7) | 3 (2.3)

The safety profile in the clinical trial of cSSSI pediatric patients was similar to that observed in the cSSSI adult patients.

S. aureus Bacteremia Trial in Pediatric Patients

The safety of daptomycin for injection was evaluated in one clinical trial (in S. aureus bacteremia), which treated 55 pediatric patients with intravenous daptomycin for injection and 26 patients with comparator agents. Patients were given age-dependent doses once daily for a treatment period of up to 42 days (mean duration of IV treatment was 12 days). The doses by age group were as follows: 12 mg/kg for 1 to <6 years, 9 mg/kg for 7 to 11 years and 7 mg/kg for 12 to 17 years of age [see Clinical Studies (14)]. Patients treated with daptomycin for injection were (69%) male and (31%) female. No patients 1 to <2 years of age were enrolled.

Adverse Reactions Leading to Discontinuation

In the bacteremia study, daptomycin for injection was discontinued in 3/55 (5.5%) patients due to an adverse reaction, while comparator was discontinued in 2/26 (7.7%) patients.

Most Common Adverse Reactions

The rates of the most common adverse reactions, organized by body system, observed in these pediatric patients with bacteremia are displayed in Table 11.

Table 11: Incidence of Adverse Reactions that Occurred in ≥5% of Pediatric Patients in the Daptomycin for Injection Treatment-Arm and Greater Than or Equal to the Comparator Treatment-Arm in the Pediatric Bacteremia Trial
Adverse Reaction | Daptomycin for Injection (N = 55) | Comparator [Comparators included intravenous therapy with either vancomycin, cefazolin, or an anti-staphylococcal semi-synthetic penicillin (nafcillin, oxacillin or cloxacillin)] (N = 26)
Adverse Reaction | n (%) | n (%)
Gastrointestinal disorders
Vomiting | 6 (10.9) | 2 (7.7)
Investigations
Blood CPK increased | 4 (7.3) | 0

6.2 Post-Marketing Experience

The following adverse reactions have been identified during post-approval use of daptomycin for injection. Because these reactions are reported voluntarily from a population of uncertain size, it is not always possible to reliably estimate their frequency or establish a causal relationship to drug exposure.

Blood and lymphatic system disorders: anemia, thrombocytopenia

General and administration site conditions: pyrexia

Immune System Disorders: anaphylaxis; hypersensitivity reactions, including angioedema, pruritus, hives, shortness of breath, difficulty swallowing, truncal erythema, and pulmonary eosinophilia [see Contraindications (4) and Warnings and Precautions (5.1)]

Infections and Infestations: Clostridioides difficile–associated diarrhea [see Warnings and Precautions (5.8)]

Laboratory Investigations: platelet count decreased

Musculoskeletal Disorders: myoglobin increased; rhabdomyolysis (some reports involved patients treated concurrently with daptomycin for injection and HMG-CoA reductase inhibitors) [see Warnings and Precautions (5.2), Drug Interactions (7.1), and Clinical Pharmacology (12.3)]

Respiratory, Thoracic, and Mediastinal Disorders: cough, eosinophilic pneumonia, organizing pneumonia [see Warnings and Precautions (5.3)]

Nervous System Disorders: peripheral neuropathy [see Warnings and Precautions (5.6)]

Skin and Subcutaneous Tissue Disorders: serious skin reactions, including drug reaction with eosinophilia and systemic symptoms (DRESS), vesiculobullous rash (with or without mucous membrane involvement, including Stevens-Johnson syndrome [SJS] and toxic epidermal necrolysis [TEN]), and acute generalized exanthematous pustulosis [see Warnings and Precautions (5.4)]

Gastrointestinal Disorders: nausea, vomiting

Metabolic and Nutritional Disorders: hyperkalemia

Renal and urinary disorders: acute kidney injury, renal insufficiency, renal failure, and tubulointerstitial nephritis (TIN) [see Warnings and Precautions (5.5)]

Special Senses: visual disturbances

7 DRUG INTERACTIONS

7.1 HMG-CoA Reductase Inhibitors

In healthy adult subjects, concomitant administration of daptomycin for injection and simvastatin had no effect on plasma trough concentrations of simvastatin, and there were no reports of skeletal myopathy [see Clinical Pharmacology (12.3)].

However, inhibitors of HMG-CoA reductase may cause myopathy, which is manifested as muscle pain or weakness associated with elevated levels of creatine phosphokinase (CPK). In the adult Phase 3 S. aureus bacteremia/endocarditis trial, some patients who received prior or concomitant treatment with an HMG-CoA reductase inhibitor developed elevated CPK [see Adverse Reactions (6.1)]. Experience with the coadministration of HMG-CoA reductase inhibitors and daptomycin for injection in patients is limited; therefore, consideration should be given to suspending use of HMG-CoA reductase inhibitors temporarily in patients receiving Daptomycin for Injection.

7.2 Drug-Laboratory Test Interactions

Clinically relevant plasma concentrations of daptomycin have been observed to cause a significant concentration-dependent false prolongation of prothrombin time (PT) and elevation of International Normalized Ratio (INR) when certain recombinant thromboplastin reagents are utilized for the assay. The possibility of an erroneously elevated PT/INR result due to interaction with a recombinant thromboplastin reagent may be minimized by drawing specimens for PT or INR testing near the time of trough plasma concentrations of daptomycin. However, sufficient daptomycin concentrations may be present at trough to cause interaction.

If confronted with an abnormally high PT/INR result in a patient being treated with Daptomycin for Injection, it is recommended that clinicians:

- Repeat the assessment of PT/INR, requesting that the specimen be drawn just prior to the next Daptomycin for Injection dose (i.e., at trough concentration). If the PT/INR value obtained at trough remains substantially elevated above what would otherwise be expected, consider evaluating PT/INR utilizing an alternative method.
- Evaluate for other causes of abnormally elevated PT/INR results.

8 USE IN SPECIFIC POPULATIONS

8.1 Pregnancy

Risk Summary

Limited published data on use of daptomycin for injection in pregnant women are insufficient to inform a drug-associated risk for major birth defects and miscarriage. In animal reproduction studies performed in rats and rabbits daptomycin was administered intravenously during organogenesis at doses 2 and 4–times, respectively, the recommended 6 mg/kg human dose (on a body surface area basis). No evidence of adverse developmental outcomes was observed.

The background risk of major birth defects and miscarriage for the indicated population is unknown. All pregnancies have a background risk of birth defect, loss, or other adverse outcomes. In the U.S. general population, the estimated background risk of major birth defects and miscarriage in clinically recognized pregnancies is 2-4% and 15-20%, respectively.

Data

Animal Data

In pregnant rats, daptomycin was administered intravenously at doses of 5, 20, or 75 mg/kg/day during the gestation days 6 to 18. Maternal body weight gain was decreased at 75 mg/kg/day. No embryo/fetal effects were noted at the highest dose of 75 mg/kg/day, a dose approximately 2-fold higher than in humans at the recommended maximum dose of 6 mg/kg (based on body surface area).

In pregnant rabbits, daptomycin was administered intravenously at doses of 5, 20, or 75 mg/kg/day during the gestation days 6 to 15. Maternal body weight gain and food consumption were decreased at 75 mg/kg/day. No embryo/fetal effects were noted at the highest dose of 75 mg/kg/day, a dose approximately 4-fold higher than in humans at the maximum recommended dose of 6 mg/kg (based on body surface area).

In a combined fertility and pre/postnatal development study, daptomycin was administered intravenously to female rats at doses of 2, 25, 75 mg/kg/day from 14-days pre-mating through lactation/postpartum day 20). No effects on pre/postnatal development were observed up to the highest dose of 75 mg/kg/day, a dose approximately 2-fold higher than the maximum recommended human dose of 6 mg/kg (based on body surface area)^1.

8.2 Lactation

Risk Summary

Limited published data report that daptomycin is present in human milk at infant doses of 0.1% of the maternal dose (see Data)^2,3,4. There is no information on the effects of daptomycin on the breastfed infant or the effects of daptomycin on milk production. The developmental and health benefits of breastfeeding should be considered along with the mother's clinical need for daptomycin for injection and any potential adverse effects on the breastfed infant from Daptomycin for Injection or from the underlying maternal condition.

8.4 Pediatric Use

The safety and effectiveness of daptomycin for injection in the treatment of cSSSI and S. aureus bloodstream infections (bacteremia) have been established in the age groups 1 to 17 years of age. Use of Daptomycin for Injection in these age groups is supported by evidence from adequate and well-controlled studies in adults, with additional data from pharmacokinetic studies in pediatric patients, and from safety, efficacy and PK studies in pediatric patients with cSSSI and S. aureus bloodstream infections [see Adverse Reactions (6.1), Clinical Pharmacology (12.3), and Clinical Studies (14.1, 14.2)].

Safety and effectiveness in pediatric patients below the age of one year have not been established. Avoid use of Daptomycin for Injection in pediatric patients younger than one year of age due to the risk of potential effects on muscular, neuromuscular, and/or nervous systems (either peripheral and/or central) observed in neonatal dogs [see Warnings and Precautions (5.7) and Nonclinical Toxicology (13.2)].

Daptomycin for Injection is not indicated in pediatric patients with renal impairment because dosage has not been established in these patients.

Daptomycin for injection has not been studied in pediatric patients with other bacterial infections.

8.5 Geriatric Use

Of the 534 adult patients treated with daptomycin for injection in Phase 3 controlled clinical trials of complicated skin and skin structure infections (cSSSI), 27% were 65 years of age or older and 12% were 75 years of age or older. Of the 120 adult patients treated with daptomycin for injection in the Phase 3 controlled clinical trial of S. aureus bacteremia/endocarditis, 25% were 65 years of age or older and 16% were 75 years of age or older. In Phase 3 adult clinical trials of cSSSI and S. aureus bacteremia/endocarditis, clinical success rates were lower in patients ≥65 years of age than in patients <65 years of age. In addition, treatment-emergent adverse events were more common in patients ≥65 years of age than in patients <65 years of age.

The exposure of daptomycin was higher in healthy elderly subjects than in healthy young adult subjects. However, no adjustment of Daptomycin for Injection dosage is warranted for elderly patients with creatinine clearance (CLCR) ≥30 mL/min [see Dosage and Administration (2.6) and Clinical Pharmacology (12.3)].

8.6 Patients with Renal Impairment

Daptomycin is eliminated primarily by the kidneys; therefore, a modification of Daptomycin for Injection dosage interval is recommended for adult patients with CLCR <30 mL/min, including patients receiving hemodialysis or continuous ambulatory peritoneal dialysis (CAPD). In adult patients with renal impairment, both renal function and creatine phosphokinase (CPK) should be monitored more frequently than once weekly [see Dosage and Administration (2.6), Warnings and Precautions (5.2, 5.10), and Clinical Pharmacology (12.3)].

The dosage regimen for Daptomycin for Injection in pediatric patients with renal impairment has not been established.

10 OVERDOSAGE

In the event of overdosage, supportive care is advised with maintenance of glomerular filtration. Daptomycin is cleared slowly from the body by hemodialysis (approximately 15% of the administered dose is removed over 4 hours) and by peritoneal dialysis (approximately 11% of the administered dose is removed over 48 hours). The use of high-flux dialysis membranes during 4 hours of hemodialysis may increase the percentage of dose removed compared with that removed by low-flux membranes.

11 DESCRIPTION

Daptomycin for Injection contains daptomycin, a cyclic lipopeptide antibacterial agent derived from the fermentation of Streptomyces roseosporus. The chemical name is N-decanoyl-L-tryptophyl-D-asparaginyl-L-aspartyl-L-threonylglycyl-L-ornithyl-L-aspartyl-D-alanyl-L-aspartylglycyl-D-seryl-threo-3-methyl-L-glutamyl-3-anthraniloyl-L-alanine ε1-lactone. The chemical structure is:

The empirical formula is C72H101N17O26; the molecular weight is 1620.67. Daptomycin for Injection is supplied in a single-dose vial as a sterile, preservative-free, pale yellow to light brown, lyophilized powder or cake containing 350 mg or 500 mg of daptomycin for intravenous (IV) use following reconstitution [see Dosage and Administration (2.7)]. Daptomycin for Injection 350 mg per vial contains 350 mg daptomycin, 188.1 mg of L-arginine, 100.5 mg of L-histidine, and 28.3 mg of L-isoleucine. Hydrochloric acid is used to adjust the pH. Daptomycin for Injection 500 mg per vial contains 500 mg daptomycin, 268.7 mg of L-arginine, 143.6 mg of L-histidine, and 40.5 mg of L-isoleucine. Hydrochloric acid is used to adjust the pH. The pH of the solution upon reconstitution is between 5.7 and 6.7. Freshly reconstituted solutions of Daptomycin for Injection range in color from pale yellow to light brown.

12 CLINICAL PHARMACOLOGY

12.1 Mechanism of Action

Daptomycin is an antibacterial drug [see Clinical Pharmacology (12.4)].

12.2 Pharmacodynamics

Based on animal models of infection, the antimicrobial activity of daptomycin appears to correlate with the AUC/MIC (area under the concentration-time curve/minimum inhibitory concentration) ratio for certain pathogens, including S. aureus. The principal pharmacokinetic/pharmacodynamic parameter best associated with clinical and microbiological cure has not been elucidated in clinical trials with daptomycin for injection.

12.3 Pharmacokinetics

Daptomycin for Injection Administered over a 30-Minute Period in Adults

The mean and standard deviation (SD) pharmacokinetic parameters of daptomycin at steady-state following intravenous (IV) administration of daptomycin for injection over a 30-minute period at 4 to 12 mg/kg every 24h to healthy young adults are summarized in Table 12.

Table 12: Mean (SD) Daptomycin Pharmacokinetic Parameters in Healthy Adult Volunteers at Steady-State
Dose [Daptomycin for injection was administered by IV infusion over a 30-minute period.] [Doses of Daptomycin for injection in excess of 6 mg/kg have not been approved.] (mg/kg) | Pharmacokinetic Parameters [AUC0-24, area under the concentration-time curve from 0 to 24 hours; t1/2, elimination half-life; Vss, volume of distribution at steady-state; CLT, total plasma clearance; Cmax, maximum plasma concentration.]
Dose [Daptomycin for injection was administered by IV infusion over a 30-minute period.] [Doses of Daptomycin for injection in excess of 6 mg/kg have not been approved.] (mg/kg) | AUC0-24 (mcg∙h/mL) | t1/2 (h) | Vss (L/kg) | CLT (mL/h/kg) | Cmax (mcg/mL)
4 (N=6) | 494 (75) | 8.1 (1.0) | 0.096 (0.009) | 8.3 (1.3) | 57.8 (3.0)
6 (N=6) | 632 (78) | 7.9 (1.0) | 0.101 (0.007) | 9.1 (1.5) | 93.9 (6.0)
8 (N=6) | 858 (213) | 8.3 (2.2) | 0.101 (0.013) | 9.0 (3.0) | 123.3 (16.0)
10 (N=9) | 1039 (178) | 7.9 (0.6) | 0.098 (0.017) | 8.8 (2.2) | 141.1 (24.0)
12 (N=9) | 1277 (253) | 7.7 (1.1) | 0.097 (0.018) | 9.0 (2.8) | 183.7 (25.0)

Daptomycin pharmacokinetics were generally linear and time-independent at daptomycin for injection doses of 4 to 12 mg/kg every 24h administered by IV infusion over a 30-minute period for up to 14 days. Steady-state trough concentrations were achieved by the third daily dose. The mean (SD) steady-state trough concentrations attained following the administration of 4, 6, 8, 10, and 12 mg/kg every 24h were 5.9 (1.6), 6.7 (1.6), 10.3 (5.5), 12.9 (2.9), and 13.7 (5.2) mcg/mL, respectively.

Daptomycin for Injection Administered over a 2-Minute Period in Adults

Following IV administration of daptomycin for injection over a 2-minute period to healthy adult volunteers at doses of 4 mg/kg (N=8) and 6 mg/kg (N=12), the mean (SD) steady-state systemic exposure (AUC) values were 475 (71) and 701 (82) mcg∙h/mL, respectively. Values for maximum plasma concentration (Cmax) at the end of the 2-minute period could not be determined adequately in this study. However, using pharmacokinetic parameters from 14 healthy adult volunteers who received a single dose of daptomycin for injection 6 mg/kg IV administered over a 30-minute period in a separate study, steady-state Cmax values were simulated for daptomycin for injection 4 and 6 mg/kg IV administered over a 2-minute period. The simulated mean (SD) steady-state Cmax values were 77.7 (8.1) and 116.6 (12.2) mcg/mL, respectively.

Distribution

Daptomycin is reversibly bound to human plasma proteins, primarily to serum albumin, in a concentration-independent manner. The overall mean binding ranges from 90 to 93%.

In clinical studies, mean serum protein binding in adult subjects with creatinine clearance (CLCR) ≥30 mL/min was comparable to that observed in healthy adult subjects with normal renal function. However, there was a trend toward decreasing serum protein binding among subjects with CLCR <30 mL/min (88%), including those receiving hemodialysis (86%) and continuous ambulatory peritoneal dialysis (CAPD) (84%). The protein binding of daptomycin in adult subjects with moderate hepatic impairment (Child-Pugh Class B) was similar to that in healthy adult subjects.

The volume of distribution at steady-state (Vss) of daptomycin in healthy adult subjects was approximately 0.1 L/kg and was independent of dose.

Metabolism

In in vitro studies, daptomycin was not metabolized by human liver microsomes.

In 5 healthy adults after infusion of radiolabeled ^14C-daptomycin, the plasma total radioactivity was similar to the concentration determined by microbiological assay. Inactive metabolites were detected in urine, as determined by the difference between total radioactive concentrations and microbiologically active concentrations. In a separate study, no metabolites were observed in plasma on Day 1 following the administration of daptomycin for injection at 6 mg/kg to adult subjects. Minor amounts of three oxidative metabolites and one unidentified compound were detected in urine. The site of metabolism has not been identified.

Excretion

Daptomycin is excreted primarily by the kidneys. In a mass balance study of 5 healthy adult subjects using radiolabeled daptomycin, approximately 78% of the administered dose was recovered from urine based on total radioactivity (approximately 52% of the dose based on microbiologically active concentrations), and 5.7% of the administered dose was recovered from feces (collected for up to 9 days) based on total radioactivity.

Specific Populations

Patients with Renal Impairment

Population-derived pharmacokinetic parameters were determined for infected adult patients (complicated skin and skin structure infections [cSSSI] and S. aureus bacteremia) and noninfected adult subjects with various degrees of renal function (Table 13). Total plasma clearance (CLT), elimination half-life (t1/2), and volume of distribution at steady-state (Vss) in patients with cSSSI were similar to those in patients with S. aureus bacteremia. Following administration of daptomycin for injection 4 mg/kg every 24h by IV infusion over a 30-minute period, the mean CLT was 9%, 22%, and 46% lower among subjects and patients with mild (CLCR 50–80 mL/min), moderate (CLCR 30– <50 mL/min), and severe (CLCR <30 mL/min) renal impairment, respectively, than in those with normal renal function (CLCR >80 mL/min). The mean steady-state systemic exposure (AUC), t1/2, and Vss increased with decreasing renal function, although the mean AUC for patients with CLCR 30–80 mL/min was not markedly different from the mean AUC for patients with normal renal function. The mean AUC for patients with CLCR <30 mL/min and for patients on dialysis (CAPD and hemodialysis dosed post-dialysis) was approximately 2 and 3 times higher, respectively, than for patients with normal renal function. The mean Cmax ranged from 60 to 70 mcg/mL in patients with CLCR ≥30 mL/min, while the mean Cmax for patients with CLCR <30 mL/min ranged from 41 to 58 mcg/mL. After administration of daptomycin for injection 6 mg/kg every 24h by IV infusion over a 30-minute period, the mean Cmax ranged from 80 to 114 mcg/mL in patients with mild to moderate renal impairment and was similar to that of patients with normal renal function.

Table 13: Mean (SD) Daptomycin Population Pharmacokinetic Parameters Following Infusion of Daptomycin for Injection 4 mg/kg or 6 mg/kg to Infected Adult Patients and Noninfected Adult Subjects with Various Degrees of Renal Function
Renal Function | Pharmacokinetic Parameters [CLCR, creatinine clearance estimated using the Cockcroft-Gault equation with actual body weight; CAPD, continuous ambulatory peritoneal dialysis; AUC0-∞, area under the concentration-time curve extrapolated to infinity; AUCss, area under the concentration-time curve calculated over the 24-hour dosing interval at steady-state; Cmin, ss trough concentration at steady-state; NA, not applicable.]
Renal Function | t1/2 [Parameters obtained following a single dose from patients with complicated skin and skin structure infections and healthy subjects.] (h) 4 mg/kg | Vss (L/kg) 4 mg/kg | CLT (mL/h/kg) 4 mg/kg | AUC0-∞ (mcg∙h/mL) 4 mg/kg | AUCss [Parameters obtained at steady-state from patients with S. aureus bacteremia.] (mcg∙h/mL) 6 mg/kg | Cmin, ss (mcg/mL) 6 mg/kg
Normal (CLCR >80 mL/min) | 9.39 (4.74) N=165 | 0.13 (0.05) N=165 | 10.9 (4.0) N=165 | 417 (155) N=165 | 545 (296) N=62 | 6.9 (3.5) N=61
Mild Renal Impairment (CLCR 50– 80 mL/min) | 10.75 (8.36) N=64 | 0.12 (0.05) N=64 | 9.9 (4.0) N=64 | 466 (177) N=64 | 637 (215) N=29 | 12.4 (5.6) N=29
Moderate Renal Impairment (CLCR 30– <50 mL/min) | 14.70 (10.50) N=24 | 0.15 (0.06) N=24 | 8.5 (3.4) N=24 | 560 (258) N=24 | 868 (349) N=15 | 19.0 (9.0) N=14
Severe Renal Impairment (CLCR <30 mL/min) | 27.83 (14.85) N=8 | 0.20 (0.15) N=8 | 5.9 (3.9) N=8 | 925 (467) N=8 | 1050 (892) N=2 | 24.4 (21.4) N=2
Hemodialysis | 30.51 (6.51) N=16 | 0.16 (0.04) N=16 | 3.9 (2.1) N=16 | 1193 (399) N=16 | NA | NA
CAPD | 27.56 (4.53) N=5 | 0.11 (0.02) N=5 | 2.9 (0.4) N=5 | 1409 (238) N=5 | NA | NA
Note: Daptomycin for injection was administered over a 30-minute period.

Because renal excretion is the primary route of elimination, adjustment of Daptomycin for Injection dosage interval is necessary in adult patients with severe renal impairment (CLCR <30 mL/min) [see Dosage and Administration (2.6)].

Patients with Hepatic Impairment

The pharmacokinetics of daptomycin were evaluated in 10 adult subjects with moderate hepatic impairment (Child-Pugh Class B) and compared with those in healthy adult volunteers (N=9) matched for gender, age, and weight. The pharmacokinetics of daptomycin were not altered in subjects with moderate hepatic impairment. No dosage adjustment is warranted when Daptomycin for Injection is administered to patients with mild to moderate hepatic impairment. The pharmacokinetics of daptomycin in patients with severe hepatic impairment (Child-Pugh Class C) have not been evaluated.

Gender

No clinically significant gender-related differences in daptomycin pharmacokinetics have been observed. No dosage adjustment is warranted based on gender when Daptomycin for Injection is administered.

Geriatric Patients

The pharmacokinetics of daptomycin were evaluated in 12 healthy elderly subjects (≥75 years of age) and 11 healthy young adult controls (18 to 30 years of age). Following administration of a single 4 mg/kg dose of daptomycin for injection by IV infusion over a 30-minute period, the mean total clearance of daptomycin was approximately 35% lower and the mean AUC0-∞ was approximately 58% higher in elderly subjects than in healthy young adult subjects. There were no differences in Cmax [see Use in Specific Populations (8.5)].

Obese Patients

The pharmacokinetics of daptomycin were evaluated in 6 moderately obese (Body Mass Index [BMI] 25 to 39.9 kg/m^2) and 6 extremely obese (BMI ≥40 kg/m^2) adult subjects and controls matched for age, gender, and renal function. Following administration of daptomycin for injection by IV infusion over a 30-minute period as a single 4 mg/kg dose based on total body weight, the total plasma clearance of daptomycin normalized to total body weight was approximately 15% lower in moderately obese subjects and 23% lower in extremely obese subjects than in nonobese controls. The AUC0-∞ of daptomycin was approximately 30% higher in moderately obese subjects and 31% higher in extremely obese subjects than in nonobese controls. The differences were most likely due to differences in the renal clearance of daptomycin. No adjustment of Daptomycin for Injection dosage is warranted in obese patients.

Pediatric Patients

The pharmacokinetics of daptomycin in pediatric subjects was evaluated in 3 single-dose pharmacokinetic studies. In general, body weight-normalized total body clearance in pediatric patients was higher than in adults and increased with a decrease of age, whereas elimination half-life tends to decrease with a decrease of age. Body weight-normalized total body clearance and elimination half-life of daptomycin in children 2 to 6 years of age were similar at different doses.

A study was conducted to assess safety, efficacy, and pharmacokinetics of daptomycin in pediatric patients (1 to 17 years old, inclusive) with cSSSI caused by Gram-positive pathogens. Patients were enrolled into 4 age groups [see Clinical Studies (14.1)], and intravenous daptomycin for injection doses of 5 to 10 mg/kg once daily were administered. Following administration of multiple doses, daptomycin exposure (AUCss and Cmax, ss) was similar across different age groups after dose adjustment based on body weight and age (Table 14).

Table 14: Mean (SD) Daptomycin Population Pharmacokinetic Parameters in cSSSI Pediatric Patients
Age | Pharmacokinetic Parameters
Age | Dose (mg/kg) | Infusion Duration (min) | AUCss (mcg∙h/mL) | t1/2 (h) | Vss (mL) | CLT (mL/h/kg) | Cmax, ss (mcg/mL)
12 to 17 years (N=6) | 5 | 30 | 434 (67.9) | 7.1 (0.9) | 8200 (3250) | 11.8 (2.15) | 76.4 (6.75)
7 to 11 years (N=2) | 7 | 30 | 543 [Mean is calculated from N=2] | 6.8 | 4470 | 13.2 | 92.4
2 to 6 years (N=7) | 9 | 60 | 452 (93.1) | 4.6 (0.8) | 2750 (832) | 20.8 (4.29) | 90.3 (14.0)
1 to less than 2 years (N=27) | 10 | 60 | 462 (138) | 4.8 (0.6) | 1670 (446) | 23.1 (5.43) | 81.6 (20.7)
AUCss, area under the concentration-time curve at steady state; CLT, clearance normalized to body weight; Vss, volume of distribution at steady state; t½, terminal half-life

A study was conducted to assess safety, efficacy, and pharmacokinetics of daptomycin in pediatric patients with S. aureus bacteremia. Patients were enrolled into 3 age groups [see Clinical Studies (14.2)], and intravenous doses of 7 to 12 mg/kg once daily were administered. Following administration of multiple doses, daptomycin exposure (AUCss and Cmax, ss) was similar across different age groups after dose adjustment based on body weight and age (Table 15).

Table 15: Mean (SD) of Daptomycin Pharmacokinetics in Bacteremia Pediatric Patients
Age | Pharmacokinetic Parameters
Age | Dose (mg/kg) | Infusion Duration (min) | AUCss (mcg∙h/mL) | t1/2 (h) | Vss (mL) | CLT (mL/h/kg) | Cmax, ss (mcg/mL)
12 to 17 years (N=13) | 7 | 30 | 656 (334) | 7.5 (2.3) | 6420 (1980) | 12.4 (3.9) | 104 (35.5)
7 to 11 years (N=19) | 9 | 30 | 579 (116) | 6.0 (0.8) | 4510 (1470) | 15.9 (2.8) | 104 (14.5)
2 to 6 years (N=19) | 12 | 60 | 620 (109) | 5.1 (0.6) | 2200 (570) | 19.9 (3.4) | 106 (12.8)
AUCss, area under the concentration-time curve at steady state; CLT, clearance normalized to body weight; Vss, volume of distribution at steady state; t½, terminal half-life

No patients 1 to <2 years of age were enrolled in the study. Simulation using a population pharmacokinetic model demonstrated that the AUCss of daptomycin in pediatric patients 1 to <2 years of age receiving 12 mg/kg once daily would be comparable to that in adult patients receiving 6 mg/kg once daily.

Drug Interaction Studies

In Vitro Studies

In vitro studies with human hepatocytes indicate that daptomycin does not inhibit or induce the activities of the following human cytochrome P450 isoforms: 1A2, 2A6, 2C9, 2C19, 2D6, 2E1, and 3A4. It is unlikely that daptomycin will inhibit or induce the metabolism of drugs metabolized by the P450 system.

Aztreonam

In a study in which 15 healthy adult subjects received a single dose of daptomycin for injection 6 mg/kg IV and a combination dose of daptomycin for injection 6 mg/kg IV and aztreonam 1 g IV, administered over a 30-minute period, the Cmax and AUC0-∞ of daptomycin were not significantly altered by aztreonam.

Tobramycin

In a study in which 6 healthy adult males received a single dose of daptomycin for injection 2 mg/kg IV, tobramycin 1 mg/kg IV, and both in combination, administered over a 30-minute period, the mean Cmax and AUC0-∞ of daptomycin were 12.7% and 8.7% higher, respectively, when daptomycin for injection was coadministered with tobramycin. The mean Cmax and AUC0-∞ of tobramycin were 10.7% and 6.6% lower, respectively, when tobramycin was coadministered with daptomycin for injection. These differences were not statistically significant. The interaction between daptomycin and tobramycin with a clinical dose of Daptomycin for Injection is unknown.

Warfarin

In 16 healthy adult subjects, administration of daptomycin for injection 6 mg/kg every 24h by IV infusion over a 30-minute period for 5 days, with coadministration of a single oral dose of warfarin (25 mg) on the 5th day, had no significant effect on the pharmacokinetics of either drug and did not significantly alter the INR (International Normalized Ratio).

Simvastatin

In 20 healthy adult subjects on a stable daily dose of simvastatin 40 mg, administration of daptomycin for injection 4 mg/kg every 24h by IV infusion over a 30-minute period for 14 days (N=10) had no effect on plasma trough concentrations of simvastatin and was not associated with a higher incidence of adverse events, including skeletal myopathy, than in subjects receiving placebo once daily (N=10) [see Warnings and Precautions (5.2) and Drug Interactions (7.1)].

Probenecid

Concomitant administration of probenecid (500 mg 4 times daily) and a single dose of daptomycin for injection 4 mg/kg by IV infusion over a 30-minute period in adults did not significantly alter the Cmax or AUC0-∞ of daptomycin.

12.4 Microbiology

Daptomycin belongs to the cyclic lipopeptide class of antibacterials. Daptomycin has clinical utility in the treatment of infections caused by aerobic, Gram-positive bacteria. The in vitro spectrum of activity of daptomycin encompasses most clinically relevant Gram-positive pathogenic bacteria.

Daptomycin exhibits rapid, concentration-dependent bactericidal activity against Gram-positive bacteria in vitro. This has been demonstrated both by time-kill curves and by MBC/MIC (minimum bactericidal concentration/minimum inhibitory concentration) ratios using broth dilution methodology. Daptomycin maintained bactericidal activity in vitro against stationary phase S. aureus in simulated endocardial vegetations. The clinical significance of this is not known.

Mechanism of Action

Daptomycin binds to bacterial cell membranes and causes a rapid depolarization of membrane potential. This loss of membrane potential causes inhibition of DNA, RNA, and protein synthesis, which results in bacterial cell death.

Resistance

The mechanism(s) of daptomycin resistance is not fully understood. Currently, there are no known transferable elements that confer resistance to daptomycin.

Interactions with Other Antibacterials

In vitro studies have investigated daptomycin interactions with other antibacterials. Antagonism, as determined by kill curve studies, has not been observed. In vitro synergistic interactions of daptomycin with aminoglycosides, β-lactam antibacterials, and rifampin have been shown against some isolates of staphylococci (including some methicillin-resistant isolates) and enterococci (including some vancomycin-resistant isolates).

Complicated Skin and Skin Structure Infection (cSSSI) Trials in Adults

The emergence of daptomycin non-susceptible isolates occurred in 2 infected patients across the set of Phase 2 and pivotal Phase 3 clinical trials of cSSSI in adult patients. In one case, a non-susceptible S. aureus was isolated from a patient in a Phase 2 trial who received daptomycin for injection at less than the protocol-specified dose for the initial 5 days of therapy. In the second case, a non-susceptible Enterococcus faecalis was isolated from a patient with an infected chronic decubitus ulcer who was enrolled in a salvage trial.

S. aureus Bacteremia/Endocarditis and Other Post-Approval Trials in Adults

In subsequent clinical trials in adult patients, non-susceptible isolates were recovered. S. aureus was isolated from a patient in a compassionate-use trial and from 7 patients in the S. aureus bacteremia/endocarditis trial [see Clinical Studies (14.2)]. An E. faecium was isolated from a patient in a vancomycin-resistant enterococci trial.

Antimicrobial Activity

Daptomycin has been shown to be active against most isolates of the following microorganisms both in vitro and in clinical infections [see Indications and Usage (1)].

- Gram-Positive Bacteria

- Enterococcus faecalis (vancomycin-susceptible isolates only)
- Staphylococcus aureus (including methicillin-resistant isolates)
- Streptococcus agalactiae
- Streptococcus dysgalactiae subsp. equisimilis
- Streptococcus pyogenes

The following in vitro data are available, but their clinical significance is unknown. At least 90 percent of the following bacteria exhibit an in vitro minimum inhibitory concentration (MIC) less than or equal to the susceptible breakpoint for daptomycin against isolates of similar genus or organism group. However, the efficacy of daptomycin in treating clinical infections caused by these bacteria has not been established in adequate and well-controlled clinical trials.

- Gram-Positive Bacteria

- Corynebacterium jeikeium
- Enterococcus faecalis (vancomycin-resistant isolates)
- Enterococcus faecium (including vancomycin-resistant isolates)
- Staphylococcus epidermidis (including methicillin-resistant isolates)
- Staphylococcus haemolyticus

Susceptibility Testing

For specific information regarding susceptibility test interpretive criteria and associated test methods and quality control standards recognized by FDA for daptomycin, please see: https://www.fda.gov/STIC.

13 NONCLINICAL TOXICOLOGY

13.1 Carcinogenesis, Mutagenesis, Impairment of Fertility

Long-term carcinogenicity studies in animals have not been conducted to evaluate the carcinogenic potential of daptomycin for injection. However, neither mutagenic nor clastogenic potential was found in a battery of genotoxicity tests, including the Ames assay, a mammalian cell gene mutation assay, a test for chromosomal aberrations in Chinese hamster ovary cells, an in vivo micronucleus assay, an in vitro DNA repair assay, and an in vivo sister chromatid exchange assay in Chinese hamsters.

Daptomycin did not affect the fertility or reproductive performance of male and female rats when administered intravenously at doses of 25, 75, or 150 mg/kg/day, which is approximately up to 9 times the estimated human exposure level based upon AUCs (or approximately up to 4 times the recommended human dose of 6 mg/kg based on body surface area comparison).

13.2 Animal Toxicology and/or Pharmacology

Adult Animals

In animals, daptomycin administration has been associated with effects on skeletal muscle. However, there were no changes in cardiac or smooth muscle. Skeletal muscle effects were characterized by microscopic degenerative/regenerative changes and variable elevations in creatine phosphokinase (CPK). No fibrosis or rhabdomyolysis was evident in repeat-dose studies up to the highest doses tested in rats (150 mg/kg/day) and dogs (100 mg/kg/day). The degree of skeletal myopathy showed no increase when treatment was extended from 1 month to up to 6 months. Severity was dose-dependent. All muscle effects, including microscopic changes, were fully reversible within 30 days following the cessation of dosing.

In adult animals, effects on peripheral nerve (characterized by axonal degeneration and frequently accompanied by significant losses of patellar reflex, gag reflex, and pain perception) were observed at daptomycin doses higher than those associated with skeletal myopathy. Deficits in the dogs' patellar reflexes were seen within 2 weeks after the start of treatment at 40 mg/kg/day (9 times the human Cmax at the 6 mg/kg/day dose), with some clinical improvement noted within 2 weeks after the cessation of dosing. However, at 75 mg/kg/day for 1 month, 7 of 8 dogs failed to regain full patellar reflex responses within a 3-month recovery period. In a separate study in dogs receiving doses of 75 and 100 mg/kg/day for 2 weeks, minimal residual histological changes were noted at 6 months after the cessation of dosing. However, recovery of peripheral nerve function was evident.

Tissue distribution studies in rats showed that daptomycin is retained in the kidney but appears to penetrate the blood-brain barrier only minimally following single and multiple doses.

Juvenile Animals

Target organs of daptomycin-related effects in 7-week-old juvenile dogs were skeletal muscle and nerve, the same target organs as in adult dogs. In juvenile dogs, nerve effects were noted at lower daptomycin blood concentrations than in adult dogs following 28 days of dosing. In contrast to adult dogs, juvenile dogs also showed evidence of effects in nerves of the spinal cord as well as peripheral nerves after 28 days of dosing. No nerve effects were noted in juvenile dogs following 14 days of dosing at doses up to 75 mg/kg/day.

Administration of daptomycin to 7-week-old juvenile dogs for 28 days at doses of 50 mg/kg/day produced minimal degenerative effects on the peripheral nerve and spinal cord in several animals, with no corresponding clinical signs. A dose of 150 mg/kg/day for 28 days produced minimal degeneration in the peripheral nerve and spinal cord as well as minimal to mild degeneration of the skeletal muscle in a majority of animals, accompanied by slight to severe muscle weakness evident in most dogs. Following a 28-day recovery phase, microscopic examination revealed recovery of the skeletal muscle and the ulnar nerve effects, but nerve degeneration in the sciatic nerve and spinal cord was still observed in all 150 mg/kg/day dogs.

Following once-daily administration of daptomycin to juvenile dogs for 28 days, microscopic effects in nerve tissue were noted at a Cmax value of 417 mcg/mL, which is approximately 3-fold less than the Cmax value associated with nerve effects in adult dogs treated once daily with daptomycin for 28 days (1308 mcg/mL).

Neonatal Animals

Neonatal dogs (4 to 31 days old) were more sensitive to daptomycin-related adverse nervous system and/or muscular system effects than either juvenile or adult dogs. In neonatal dogs, adverse nervous system and/or muscular system effects were associated with a Cmax value approximately 3-fold less than the Cmax in juvenile dogs, and 9-fold less than the Cmax in adult dogs following 28 days of dosing. At a dose of 25 mg/kg/day with associated Cmax and AUCinf values of 147 mcg/mL and 717 mcg∙h/mL, respectively (1.6 and 1.0-fold the adult human Cmax and AUC, respectively, at the 6 mg/kg/day dose), mild clinical signs of twitching and one incidence of muscle rigidity were observed with no corresponding effect on body weight. These effects were found to be reversible within 28 days after treatment had stopped.

At higher dose levels of 50 and 75 mg/kg/day with associated Cmax and AUCinf values of ≥321 mcg/mL and ≥1470 mcg∙h/mL, respectively, marked clinical signs of twitching, muscle rigidity in the limbs, and impaired use of limbs were observed. Resulting decreases in body weights and overall body condition at doses ≥50 mg/kg/day necessitated early discontinuation by postnatal day (PND) 19.

Histopathological assessment did not reveal any daptomycin-related changes in the peripheral and central nervous system tissue, as well as in the skeletal muscle or other tissues assessed, at any dose level.

No adverse effects were observed in the dogs that received daptomycin at 10 mg/kg/day, the NOAEL, with associated Cmax and AUCinf values of 62 mcg/mL and 247 mcg∙h/mL, respectively (or 0.6 and 0.4-fold the adult human Cmax and AUC, respectively at the 6 mg/kg dose).

14 CLINICAL STUDIES

14.1 Complicated Skin and Skin Structure Infections

Adults with cSSSI

Adult patients with clinically documented complicated skin and skin structure infections (cSSSI) (Table 16) were enrolled in two randomized, multinational, multicenter, investigator-blinded trials comparing daptomycin for injection (4 mg/kg IV every 24h) with either vancomycin (1 g IV q12h) or an anti-staphylococcal semisynthetic penicillin (i.e., nafcillin, oxacillin, cloxacillin, or flucloxacillin; 4 to 12 g IV per day). Patients could switch to oral therapy after a minimum of 4 days of IV treatment if clinical improvement was demonstrated. Patients known to have bacteremia at baseline were excluded. Patients with creatinine clearance (CLCR) between 30 and 70 mL/min were to receive a lower dose of daptomycin for injection as specified in the protocol; however, the majority of patients in this subpopulation did not have the dose of daptomycin for injection adjusted.

Table 16: Investigator's Primary Diagnosis in the cSSSI Trials in Adult Patients (Population: ITT)
Primary Diagnosis | Adult Patients (Daptomycin for Injection / Comparator [Comparator: vancomycin (1 g IV q12h) or an anti-staphylococcal semi-synthetic penicillin (i.e., nafcillin, oxacillin, cloxacillin, or flucloxacillin; 4 to 12 g/day IV in divided doses).])
Primary Diagnosis | Study 9801 N=264 / N=266 | Study 9901 N=270 / N=292 | Pooled N=534 / N=558
Wound Infection | 99 (38%) / 116 (44%) | 102 (38%) / 108 (37%) | 201 (38%) / 224 (40%)
Major Abscess | 55 (21%) / 43 (16%) | 59 (22%) / 65 (22%) | 114 (21%) / 108 (19%)
Ulcer Infection | 71 (27%) / 75 (28%) | 53 (20%) / 68 (23%) | 124 (23%) / 143 (26%)
Other Infection [The majority of cases were subsequently categorized as complicated cellulitis, major abscesses, or traumatic wound infections.] | 39 (15%) / 32 (12%) | 56 (21%) / 51 (18%) | 95 (18%) / 83 (15%)

One trial was conducted primarily in the United States and South Africa (study 9801), and the second was conducted at non-US sites only (study 9901). The two trials were similar in design but differed in patient characteristics, including history of diabetes and peripheral vascular disease. There were a total of 534 adult patients treated with daptomycin for injection and 558 treated with comparator in the two trials. The majority (89.7%) of patients received IV medication exclusively.

The efficacy endpoints in both trials were the clinical success rates in the intent-to-treat (ITT) population and in the clinically evaluable (CE) population. In study 9801, clinical success rates in the ITT population were 62.5% (165/264) in patients treated with daptomycin for injection and 60.9% (162/266) in patients treated with comparator drugs. Clinical success rates in the CE population were 76.0% (158/208) in patients treated with daptomycin for injection and 76.7% (158/206) in patients treated with comparator drugs. In study 9901, clinical success rates in the ITT population were 80.4% (217/270) in patients treated with daptomycin for injection and 80.5% (235/292) in patients treated with comparator drugs. Clinical success rates in the CE population were 89.9% (214/238) in patients treated with daptomycin for injection and 90.4% (226/250) in patients treated with comparator drugs.

The success rates by pathogen for microbiologically evaluable patients are presented in Table 17.

Table 17: Clinical Success Rates by Infecting Pathogen in the cSSSI Trials in Adult Patients (Population: Microbiologically Evaluable)
Pathogen | Success Rate n/N (%)
Pathogen | Daptomycin for Injection | Comparator [Comparator: vancomycin (1 g IV q12h) or an anti-staphylococcal semi-synthetic penicillin (i.e., nafcillin, oxacillin, cloxacillin, or flucloxacillin; 4 to 12 g/day IV in divided doses).]
Methicillin-susceptible Staphylococcus aureus (MSSA) [As determined by the central laboratory.] | 170/198 (86%) | 180/207 (87%)
Methicillin-resistant Staphylococcus aureus (MRSA) | 21/28 (75%) | 25/36 (69%)
Streptococcus pyogenes | 79/84 (94%) | 80/88 (91%)
Streptococcus agalactiae | 23/27 (85%) | 22/29 (76%)
Streptococcus dysgalactiae subsp. equisimilis | 8/8 (100%) | 9/11 (82%)
Enterococcus faecalis (vancomycin-susceptible only) | 27/37 (73%) | 40/53 (76%)

Pediatric Patients (1 to 17 Years of Age) with cSSSI

The cSSSI pediatric trial was a single prospective multi-center, randomized, comparative trial. A total of 396 pediatric patients aged 1 to 17 years with cSSSI caused by Gram positive pathogens were enrolled into the study. Patients known to have bacteremia, osteomyelitis, endocarditis, and pneumonia at baseline were excluded. Patients were enrolled in a stepwise approach into four age groups and given age-dependent doses of daptomycin for injection once daily for up to 14 days. The different age groups and doses evaluated were as follows: Adolescents (12 to 17 years) treated with 5 mg/kg of daptomycin for injection (n=113), Children (7 to 11 years) treated with 7 mg/kg of daptomycin for injection (n=113), Children (2 to 6 years) treated with 9 mg/kg of daptomycin for injection (n=125) and Infants (1 to <2 years) treated with 10 mg/kg (n=45).

Patients were randomized 2:1 to receive daptomycin for injection or a standard of care (SOC) comparator, which included intravenous therapy with either vancomycin, clindamycin, or an anti-staphylococcal semi-synthetic penicillin (nafcillin, oxacillin, or cloxacillin). Patients could switch to oral therapy after clinical improvement was demonstrated (no minimum IV dosing was required).

The primary objective of this study was to evaluate the safety of daptomycin for injection. The clinical outcome was determined by resolution or improvement of symptoms at the End-of-Treatment (EOT), 3 days after the last dose, and Test-of-Cure (TOC), 7-14 days after the last dose. Investigator observed outcomes were verified in a blinded fashion. Of the 396 subjects randomized in the study, 389 subjects were treated with daptomycin for injection or comparator and included in the ITT population. Of these, 257 subjects were randomized to the daptomycin for injection group and 132 subjects were randomized to the comparator group. Approximately 95% of subjects switched to oral therapy. The mean day of switch was day 4, and ranged from day 1 to day 14. The clinical success rates determined at 7–14 days after last dose of therapy (IV and oral) (TOC visit) were 88% (227/257) for daptomycin for injection and 86% (114/132) for comparator.

14.2 S. aureus Bacteremia/Endocarditis

Adults with S. aureus Bacteremia/Endocarditis

The efficacy of daptomycin for injection in the treatment of adult patients with S. aureus bacteremia was demonstrated in a randomized, controlled, multinational, multicenter, open-label trial. In this trial, adult patients with at least one positive blood culture for S. aureus obtained within 2 calendar days prior to the first dose of study drug and irrespective of source were enrolled and randomized to either daptomycin for injection (6 mg/kg IV every 24h) or standard of care [an anti-staphylococcal semi-synthetic penicillin 2 g IV q4h (nafcillin, oxacillin, cloxacillin, or flucloxacillin) or vancomycin 1 g IV q12h, each with initial gentamicin 1 mg/kg IV every 8 hours for first 4 days]. Of the patients in the comparator group, 93% received initial gentamicin for a median of 4 days, compared with 1 patient (<1%) in the daptomycin for injection group. Patients with prosthetic heart valves, intravascular foreign material that was not planned for removal within 4 days after the first dose of study medication, severe neutropenia, known osteomyelitis, polymicrobial bloodstream infections, creatinine clearance <30 mL/min, and pneumonia were excluded.

Upon entry, patients were classified for likelihood of endocarditis using the modified Duke criteria (Possible, Definite, or Not Endocarditis). Echocardiography, including a transesophageal echocardiogram (TEE), was performed within 5 days following study enrollment. The choice of comparator agent was based on the oxacillin susceptibility of the S. aureus isolate. The duration of study treatment was based on the investigator's clinical diagnosis. Final diagnoses and outcome assessments at Test of Cure (6 weeks after the last treatment dose) were made by a treatment-blinded Adjudication Committee, using protocol-specified clinical definitions and a composite primary efficacy endpoint (clinical and microbiological success) at the Test of Cure visit.

A total of 246 patients ≥18 years of age (124 daptomycin for injection, 122 comparator) with S. aureus bacteremia were randomized from 48 centers in the US and Europe. In the ITT population, 120 patients received daptomycin for injection and 115 received comparator (62 received an anti-staphylococcal semi-synthetic penicillin and 53 received vancomycin). Thirty-five patients treated with an anti-staphylococcal semi-synthetic penicillin received vancomycin initially for 1 to 3 days, pending final susceptibility results for the S. aureus isolates. The median age among the 235 patients in the ITT population was 53 years (range: 21 to 91 years); 30/120 (25%) in the daptomycin for injection group and 37/115 (32%) in the comparator group were ≥65 years of age. Of the 235 ITT patients, there were 141 (60%) males and 156 (66%) Caucasians across the two treatment groups. In addition, 176 (75%) of the ITT population had systemic inflammatory response syndrome (SIRS) at baseline and 85 (36%) had surgical procedures within 30 days prior to onset of the S. aureus bacteremia. Eighty-nine patients (38%) had bacteremia caused by methicillin-resistant S. aureus (MRSA). Entry diagnosis was based on the modified Duke criteria and comprised 37 (16%) Definite, 144 (61%) Possible, and 54 (23%) Not Endocarditis. Of the 37 patients with an entry diagnosis of Definite Endocarditis, all (100%) had a final diagnosis of infective endocarditis, and of the 144 patients with an entry diagnosis of Possible Endocarditis, 15 (10%) had a final diagnosis of infective endocarditis as assessed by the Adjudication Committee. Of the 54 patients with an entry diagnosis of Not Endocarditis, 1 (2%) had a final diagnosis of infective endocarditis as assessed by the Adjudication Committee.

In the ITT population, there were 182 patients with bacteremia and 53 patients with infective endocarditis as assessed by the Adjudication Committee, including 35 with right-sided endocarditis and 18 with left-sided endocarditis. The 182 patients with bacteremia comprised 121 with complicated S. aureus bacteremia and 61 with uncomplicated S. aureus bacteremia.

Complicated bacteremia was defined as S. aureus isolated from blood cultures obtained on at least 2 different calendar days, and/or metastatic foci of infection (deep tissue involvement), and classification of the patient as not having endocarditis according to the modified Duke criteria. Uncomplicated bacteremia was defined as S. aureus isolated from blood culture(s) obtained on a single calendar day, no metastatic foci of infection, no infection of prosthetic material, and classification of the patient as not having endocarditis according to the modified Duke criteria. The definition of right-sided infective endocarditis (RIE) used in the clinical trial was Definite or Possible Endocarditis according to the modified Duke criteria and no echocardiographic evidence of predisposing pathology or active involvement of either the mitral or aortic valve. Complicated RIE comprised patients who were not intravenous drug users, had a positive blood culture for MRSA, serum creatinine ≥2.5 mg/dL, or evidence of extrapulmonary sites of infection. Patients who were intravenous drug users, had a positive blood culture for methicillin-susceptible S. aureus (MSSA), had serum creatinine <2.5 mg/dL, and were without evidence of extrapulmonary sites of infection were considered to have uncomplicated RIE.

The coprimary efficacy endpoints in the trial were the Adjudication Committee success rates at the Test of Cure visit (6 weeks after the last treatment dose) in the ITT and Per Protocol (PP) populations. The overall Adjudication Committee success rates in the ITT population were 44.2% (53/120) in patients treated with daptomycin for injection and 41.7% (48/115) in patients treated with comparator (difference = 2.4% [95% CI −10.2, 15.1]). The success rates in the PP population were 54.4% (43/79) in patients treated with daptomycin for injection and 53.3% (32/60) in patients treated with comparator (difference = 1.1% [95% CI −15.6, 17.8]).

Adjudication Committee success rates are shown in Table 18.

Table 18: Adjudication Committee Success Rates at Test of Cure in the S. aureus Bacteremia/Endocarditis Trial in Adult Patients (Population: ITT)
Population | Success Rate n/N (%) |  | Difference: Daptomycin for Injection−Comparator (Confidence Interval)
Population | Daptomycin for Injection 6 mg/kg | Comparator [Comparator: vancomycin (1 g IV q12h) or an anti-staphylococcal semi-synthetic penicillin (i.e., nafcillin, oxacillin, cloxacillin, or flucloxacillin; 2 g IV q4h), each with initial low-dose gentamicin.] | Difference: Daptomycin for Injection−Comparator (Confidence Interval)
Overall | 53/120 (44%) | 48/115 (42%) | 2.4% (−10.2, 15.1) [95% Confidence Interval]
Baseline Pathogen
Methicillin-susceptible S. aureus | 33/74 (45%) | 34/70 (49%) | −4.0% (−22.6, 14.6) [97.5% Confidence Interval (adjusted for multiplicity)]
Methicillin-resistant S. aureus | 20/45 (44%) | 14/44 (32%) | 12.6% (−10.2, 35.5)
Entry Diagnosis [According to the modified Duke criteria^5]
Definite or Possible Infective Endocarditis | 41/90 (46%) | 37/91 (41%) | 4.9% (−11.6, 21.4)
Not Infective Endocarditis | 12/30 (40%) | 11/24 (46%) | −5.8% (−36.2, 24.5)
Final Diagnosis
Uncomplicated Bacteremia | 18/32 (56%) | 16/29 (55%) | 1.1% (−31.7, 33.9) [99% Confidence Interval (adjusted for multiplicity)]
Complicated Bacteremia | 26/60 (43%) | 23/61 (38%) | 5.6% (−17.3, 28.6)
Right-Sided Infective Endocarditis | 8/19 (42%) | 7/16 (44%) | −1.6% (−44.9, 41.6)
Uncomplicated Right-Sided Infective Endocarditis | 3/6 (50%) | 1/4 (25%) | 25.0% (−51.6, 100.0)
Complicated Right-Sided Infective Endocarditis | 5/13 (39%) | 6/12 (50%) | −11.5% (−62.4, 39.4)
Left-Sided Infective Endocarditis | 1/9 (11%) | 2/9 (22%) | −11.1% (−55.9, 33.6)

Eighteen (18/120) patients in the daptomycin for injection arm and 19/116 patients in the comparator arm died during the trial. These comprise 3/28 daptomycin for injection-treated patients and 8/26 comparator-treated patients with endocarditis, as well as 15/92 daptomycin for injection-treated patients and 11/90 comparator-treated patients with bacteremia. Among patients with persisting or relapsing S. aureus infections, 8/19 daptomycin for injection-treated patients and 7/11 comparator-treated patients died.

Overall, there was no difference in time to clearance of S. aureus bacteremia between daptomycin for injection and comparator. The median time to clearance in patients with MSSA was 4 days and in patients with MRSA was 8 days.

Failure of treatment due to persisting or relapsing S. aureus infections was assessed by the Adjudication Committee in 19/120 (16%) daptomycin for injection-treated patients (12 with MRSA and 7 with MSSA) and 11/115 (10%) comparator-treated patients (9 with MRSA treated with vancomycin and 2 with MSSA treated with an anti-staphylococcal semi-synthetic penicillin). Among all failures, isolates from 6 daptomycin for injection-treated patients and 1 vancomycin-treated patient developed increasing MICs (reduced susceptibility) by central laboratory testing during or following therapy. Most patients who failed due to persisting or relapsing S. aureus infection had deep-seated infection and did not receive necessary surgical intervention [see Warnings and Precautions (5.9)].

Pediatric Patients (1 to 17 Years of Age) with S. aureus Bacteremia

The pediatric S. aureus bacteremia study was designed as a prospective multi-center, randomized, comparative trial to treat pediatric patients aged 1 to 17 years with bacteremia. Patients known to have endocarditis or pneumonia at baseline were excluded. Patients were enrolled in a stepwise approach into three age groups and given age-dependent doses of daptomycin for injection once daily for up to 42 days. The different age groups and doses evaluated were as follows: Adolescents (12 to 17 years, n=14 patients) treated with daptomycin for injection dosed at 7 mg/kg once daily, Children (7 to 11 years, n=19 patients) treated with daptomycin for injection dosed at 9 mg/kg once daily and Children (2 to 6 years, n=22 patients) treated with daptomycin for injection dosed at 12 mg/kg once daily. No patients 1 to <2 years of age were enrolled.

Patients were randomized 2:1 to receive daptomycin for injection or a standard of care comparator, which included intravenous therapy with vancomycin, semi-synthetic penicillin, first generation cephalosporin or clindamycin. Patients could switch to oral therapy after clinical improvement was demonstrated (no minimum IV dosing was required).

The primary objective of this study was to assess the safety of daptomycin for injection. The clinical outcome was determined by resolution or improvement of symptoms at test-of-cure (TOC) visit, 7 to 14 days after the last dose, which was assessed by the site level Blinded Evaluator.

Of the 82 subjects randomized in the study, 81 subjects were treated with daptomycin for injection or comparator and included in the safety population, and 73 had a proven S. aureus bacteremia at Baseline. Of these, 51 subjects were randomized to the daptomycin for injection group and 22 subjects were randomized to the comparator group. The mean duration of IV therapy was 12 days, with a range of 1 to 44 days. Forty-eight subjects switched to oral therapy, and the mean duration of oral therapy was 21 days. The clinical success rates determined at 7 to 14 days after last dose of therapy (IV and oral) (TOC visit) were 88% (45/51) for daptomycin for injection and 77% (17/22) for comparator.

15 REFERENCES

1. Liu SL, Howard LC, Van Lier RBL, Markham JK: Teratology studies with daptomycin administered intravenously (iv) to rats and rabbits. Teratology 37(5):475, 1988.
2. Stroup JS, Wagner J, Badzinski T: Use of daptomycin in a pregnant patient with Staphylococcus aureus endocarditis. Ann Pharmacother 44(4):746-749, 2010.
3. Buitrago MI, Crompton JA, Bertolami S, North DS, Nathan RA. Extremely low excretion of daptomycin into breast milk of a nursing mother with methicillin-resistant Staphylococcus aureus pelvic inflammatory disease. Pharmacotherapy 2009;29(3):347–351.
4. Klibanov OM, Vickery S, Nortey C: Successful treatment of infective panniculitis with daptomycin in a pregnant, morbidly obese patient. Ann Pharmacother 48(5):652-655, 2014.
5. Li JS, Sexton DJ, Mick N, Nettles R, Fowler VG Jr, Ryan T, Bashore T, Corey GR. Proposed modifications to the Duke criteria for the diagnosis of infective endocarditis. Clin Infect Dis 2000; 30:633–638.

16 HOW SUPPLIED/STORAGE AND HANDLING

Daptomycin for Injection is supplied as a sterile pale yellow to light brown lyophilized powder or cake in a single-dose vial containing either 350 mg or 500 mg of daptomycin:

Unit of Sale | Strength
NDC 0143-9456-01 Carton containing 1 single-dose vial | 350 mg/vial
NDC 0143-9445-01 Carton containing 1 single-dose vial | 500 mg/vial

STORAGE AND HANDLING

Store original packages at 20°C to 25°C (68°F to 77°F); excursions permitted to 15°C to 30°C (59°F to 86°F) [see USP Controlled Room Temperature]. Storage conditions for the reconstituted and diluted solutions are described in another section of the prescribing information [see Dosage and Administration (2.7)].

17 PATIENT COUNSELING INFORMATION

Allergic Reactions

Advise patients that allergic reactions, including serious skin, kidney, lung, or other organ reactions, could occur and that these serious reactions require immediate treatment. Patients should report any previous allergic reactions to daptomycin [see Warnings and Precautions (5.1, 5.4, 5.5)].

Muscle Pain or Weakness (Myopathy and Rhabdomyolysis, Peripheral Neuropathy)

Advise patients to report muscle pain or weakness, especially in the forearms and lower legs, as well as tingling or numbness [see Warnings and Precautions (5.2, 5.6)].

Cough, Breathlessness or Fever (Eosinophilic Pneumonia)

Advise patients to report any symptoms of cough, breathlessness, or fever [see Warnings and Precautions (5.3)].

C. difficile-Associated Diarrhea (CDAD)

Advise patients that diarrhea is a common problem caused by antibacterials, including Daptomycin for Injection, that usually ends when the antibacterial is discontinued. Sometimes after starting treatment with antibacterials, including Daptomycin for Injection, patients can develop watery and bloody stools (with or without stomach cramps and fever), even as late as 2 or more months after having received the last dose of the antibacterial. If this occurs, patients should contact their physician as soon as possible [see Warnings and Precautions (5.8)].

Antibacterial Resistance

Patients should be counseled that antibacterial drugs, including Daptomycin for Injection, should be used to treat bacterial infections. They do not treat viral infections (e.g., the common cold). When Daptomycin for Injection is prescribed to treat a bacterial infection, patients should be told that although it is common to feel better early in the course of therapy, the medication should be administered exactly as directed. Skipping doses or not completing the full course of therapy may (1) decrease the effectiveness of the immediate treatment and (2) increase the likelihood that bacteria will develop resistance and will not be treatable by Daptomycin for Injection or other antibacterial drugs in the future.

Manufactured for:
Hikma Pharmaceuticals USA Inc.
Berkeley Heights, NJ 07922

Made in India

Code No: AP/DRUGS/103/97

1313001199-00

PRINCIPAL DISPLAY PANEL - 350 mg Vial Carton

NDC 0143-9456-01

Rx Only

For Intravenous Use

Daptomycin
for Injection

350 mg/vial

Single-Dose Vial

Discard Unused Portion

PRINCIPAL DISPLAY PANEL - 500 mg Vial Carton

NDC 0143-9445-01

Rx Only

For Intravenous Use

Daptomycin
for Injection

500 mg/vial

Single-Dose Vial

Discard Unused Portion